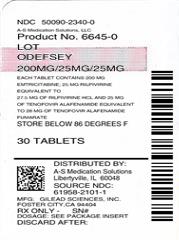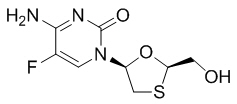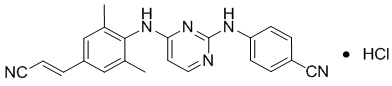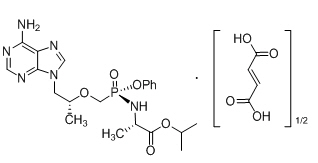 DRUG LABEL: ODEFSEY
NDC: 50090-2340 | Form: TABLET
Manufacturer: A-S Medication Solutions
Category: prescription | Type: HUMAN PRESCRIPTION DRUG LABEL
Date: 20180110

ACTIVE INGREDIENTS: EMTRICITABINE 200 mg/1 1; RILPIVIRINE HYDROCHLORIDE 25 mg/1 1; TENOFOVIR ALAFENAMIDE FUMARATE 25 mg/1 1
INACTIVE INGREDIENTS: LACTOSE MONOHYDRATE; MICROCRYSTALLINE CELLULOSE; POVIDONE, UNSPECIFIED; POLYSORBATE 20; CROSCARMELLOSE SODIUM; MAGNESIUM STEARATE; WATER; POLYVINYL ALCOHOL, UNSPECIFIED; TITANIUM DIOXIDE; POLYETHYLENE GLYCOL, UNSPECIFIED; TALC; FERROSOFERRIC OXIDE

HIGHLIGHTS OF PRESCRIBING INFORMATION

These highlights do not include all the information needed to use ODEFSEY safely and effectively. See full prescribing information for ODEFSEY.
ODEFSEY® (emtricitabine, rilpivirine, and tenofovir alafenamide) tablets, for oral use
Initial U.S. Approval: 2016

WARNING: POST TREATMENT ACUTE EXACERBATION OF HEPATITIS B

See full prescribing information for complete boxed warning.

- ODEFSEY is not approved for the treatment of chronic hepatitis B virus (HBV) infection. Severe acute exacerbations of hepatitis B have been reported in patients who are coinfected with HIV-1 and HBV and have discontinued products containing emtricitabine (FTC) and/or tenofovir disoproxil fumarate (TDF), and may occur with discontinuation of ODEFSEY. Hepatic function should be monitored closely in these patients. If appropriate, initiation of anti-hepatitis B therapy may be warranted. (5.1)

RECENT MAJOR CHANGES

- Boxed Warning, Lactic Acidosis/Severe Hepatomegaly with Steatosis [removed] | 04/2017
- Warnings and Precautions, Lactic Acidosis/Severe Hepatomegaly with Steatosis (5.9) | 04/2017
- Warnings and Precautions, Fat Redistribution [removed] | 04/2017
- Warnings and Precautions, Bone Loss and Mineralization Defects [removed] | 08/2017

1 INDICATIONS AND USAGE

ODEFSEY is a three-drug combination of emtricitabine (FTC) and tenofovir alafenamide (TAF), both HIV nucleoside analog reverse transcriptase inhibitors (NRTIs), and rilpivirine (RPV), a non-nucleoside reverse transcriptase inhibitor (NNRTI), and is indicated as a complete regimen for the treatment of HIV-1 infection in patients 12 years of age and older as initial therapy in those with no antiretroviral treatment history with HIV-1 RNA less than or equal to 100,000 copies per mL; or to replace a stable antiretroviral regimen in those who are virologically-suppressed (HIV-1 RNA less than 50 copies per mL) for at least six months with no history of treatment failure and no known substitutions associated with resistance to the individual components of ODEFSEY. (1)

2 DOSAGE AND ADMINISTRATION

- Testing: Prior to initiation of ODEFSEY, patients should be tested for hepatitis B virus infection. Assess serum creatinine, serum phosphorus, estimated creatinine clearance, urine glucose, and urine protein before initiating ODEFSEY and during therapy in all patients as clinically appropriate. (2.1)
- Recommended dosage: one tablet taken orally once daily with a meal. (2.2)
- After initiation of ODEFSEY, additional monitoring of HIV-1 RNA and regimen tolerability is recommended after replacing therapy to assess for potential virologic failure or rebound. (2.3)
- Renal impairment: ODEFSEY is not recommended in patients with estimated creatinine clearance below 30 mL per minute. (2.4)

3 DOSAGE FORMS AND STRENGTHS

Tablets: 200 mg of FTC, 25 mg of RPV and 25 mg of TAF. (3)

4 CONTRAINDICATIONS

ODEFSEY is contraindicated when coadministered with drugs where significant decreases in RPV plasma concentrations may occur, which may result in loss of virologic response and possible resistance and cross-resistance. (4)

5 WARNINGS AND PRECAUTIONS

- Skin and Hypersensitivity Reactions: Severe skin and hypersensitivity reactions have been reported during postmarketing experience with RPV-containing regimens, including cases of Drug Reaction with Eosinophilia and Systemic Symptoms (DRESS). Immediately discontinue treatment if hypersensitivity or rash with systemic symptoms or elevations in hepatic serum biochemistries develops and closely monitor clinical status, including hepatic serum biochemistries. (5.2)
- Concomitant use of ODEFSEY with other drugs that may reduce the exposure of RPV may lead to loss of therapeutic effect of ODEFSEY and possible development of resistance. (5.3)
- Concomitant use of ODEFSEY with drugs with a known risk to prolong the QTc interval of the electrocardiogram may increase the risk of Torsade de Pointes. (5.4)
- Depressive disorders: Severe depressive disorders have been reported. Immediate medical evaluation is recommended for severe depressive disorders. (5.5)
- Hepatotoxicity: Hepatic adverse events have been reported in patients receiving an RPV-containing regimen. Monitor liver-associated tests before and during treatment with ODEFSEY in patients with underlying hepatic disease or marked elevations in liver-associated tests. Also consider monitoring liver-associated tests in patients without risk factors. (5.6)
- Immune reconstitution syndrome: May necessitate further evaluation and treatment. (5.7)
- New onset or worsening renal impairment: Assessment of serum creatinine, serum phosphorus, estimated creatinine clearance, urine glucose, and urine protein is recommended before initiating ODEFSEY therapy and during therapy as clinically appropriate. (5.8)
- Lactic acidosis/severe hepatomegaly with steatosis: Discontinue treatment in patients who develop symptoms or laboratory findings suggestive of lactic acidosis or pronounced hepatotoxicity. (5.9)

6 ADVERSE REACTIONS

Most common adverse reactions (incidence greater than or equal to 2%, all grades) are headache and sleep disturbances. (6.1)

To report SUSPECTED ADVERSE REACTIONS, contact Gilead Sciences, Inc. at 1-800-GILEAD-5 or FDA at 1-800-FDA-1088 or www.fda.gov/medwatch.

7 DRUG INTERACTIONS

- CYP3A4 inducers or inhibitors: Drugs that induce or inhibit CYP3A4 may affect the plasma concentrations of RPV. (7.1)
- P-glycoprotein (P-gp) inducers or inhibitors: Drugs that strongly affect P-gp activity may lead to changes in TAF absorption. (7.1)
- Drugs that increase gastric pH: Drugs that increase gastric pH may decrease plasma concentrations of RPV. (7.1)

8 USE IN SPECIFIC POPULATIONS

- Lactation: Women infected with HIV should be instructed not to breastfeed, due to the potential for HIV transmission. (8.2)
- Pediatrics: Not recommended for patients less than 12 years of age or weighing less than 35 kg. (8.4)

FULL PRESCRIBING INFORMATION

WARNING: POST TREATMENT ACUTE EXACERBATION OF HEPATITIS B

ODEFSEY is not approved for the treatment of chronic hepatitis B virus (HBV) infection, and the safety and efficacy of ODEFSEY have not been established in patients coinfected with human immunodeficiency virus-1 (HIV-1) and HBV. Severe acute exacerbations of hepatitis B have been reported in patients who are coinfected with HIV-1 and HBV and have discontinued products containing emtricitabine (FTC) and/or tenofovir disoproxil fumarate (TDF), and may occur with discontinuation of ODEFSEY.

Hepatic function should be monitored closely with both clinical and laboratory follow-up for at least several months in patients who are coinfected with HIV-1 and HBV and discontinue ODEFSEY. If appropriate, initiation of anti-hepatitis B therapy may be warranted [see Warnings and Precautions (5.1)].

1 INDICATIONS AND USAGE

ODEFSEY is indicated as a complete regimen for the treatment of HIV-1 infection in patients 12 years of age and older as initial therapy in those with no antiretroviral treatment history with HIV-1 RNA less than or equal to 100,000 copies per mL; or to replace a stable antiretroviral regimen in those who are virologically-suppressed (HIV-1 RNA less than 50 copies per mL) for at least six months with no history of treatment failure and no known substitutions associated with resistance to the individual components of ODEFSEY [see Microbiology (12.4) and Clinical Studies (14)].

2 DOSAGE AND ADMINISTRATION

2.1 Testing Prior to Initiation of ODEFSEY

Prior to initiation of ODEFSEY, patients should be tested for hepatitis B virus infection [see Warnings and Precautions (5.1)].

It is recommended that serum creatinine, serum phosphorus, estimated creatinine clearance, urine glucose, and urine protein should be assessed before initiating ODEFSEY and during therapy in all patients as clinically appropriate [see Warnings and Precautions (5.8)].

2.2 Recommended Dosage

ODEFSEY is a 3-drug fixed dose combination product containing 200 mg of emtricitabine (FTC), 25 mg of rilpivirine (RPV), and 25 mg of tenofovir alafenamide (TAF). The recommended dosage of ODEFSEY is one tablet taken orally once daily with a meal in the following patient population: adults and in pediatric patients 12 years of age and older with body weight greater than or equal to 35 kg and a creatinine clearance greater than or equal to 30 mL per minute [see Clinical Pharmacology (12.3)].

2.3 Testing After Initiation of ODEFSEY

In virologically-suppressed patients, additional monitoring of HIV-1 RNA and regimen tolerability is recommended after replacing therapy to assess for potential virologic failure or rebound [see Clinical Studies (14)].

2.4 Not Recommended in Patients with Severe Renal Impairment

ODEFSEY is not recommended in patients with estimated creatinine clearance below 30 mL per minute [see Warnings and Precautions (5.8) and Use in Specific Populations (8.6)].

3 DOSAGE FORMS AND STRENGTHS

Each ODEFSEY tablet contains 200 mg of emtricitabine (FTC), 25 mg of rilpivirine (RPV) (equivalent to 27.5 mg of rilpivirine hydrochloride), and 25 mg of tenofovir alafenamide (TAF) (equivalent to 28 mg of tenofovir alafenamide fumarate).

The tablets are gray, capsule-shaped, film-coated and debossed with "GSI" on one side and "255" on the other side.

4 CONTRAINDICATIONS

ODEFSEY is contraindicated when coadministered with the following drugs; coadministration may result in loss of virologic response and possible resistance to ODEFSEY or to the class of NNRTIs [see Warnings and Precautions (5.3), Drug Interactions (7) and Clinical Pharmacology (12.3)]:

- the anticonvulsants carbamazepine, oxcarbazepine, phenobarbital, phenytoin
- the antimycobacterials rifampin and rifapentine
- proton pump inhibitors, such as dexlansoprazole, esomeprazole, lansoprazole, omeprazole, pantoprazole, rabeprazole
- the glucocorticoid systemic dexamethasone (more than a single dose)
- St. John's wort (Hypericum perforatum)

5 WARNINGS AND PRECAUTIONS

5.1 Severe Acute Exacerbation of Hepatitis B in Patients Coinfected with HIV-1 and HBV

Patients with HIV-1 should be tested for the presence of hepatitis B virus (HBV) before initiating antiretroviral therapy [see Dosage and Administration (2.1)]. ODEFSEY is not approved for the treatment of chronic HBV infection, and the safety and efficacy of ODEFSEY have not been established in patients coinfected with HIV-1 and HBV.

Severe acute exacerbations of hepatitis B (e.g., liver decompensation and liver failure) have been reported in patients who are coinfected with HIV-1 and HBV and have discontinued products containing FTC and/or TDF, and may occur with discontinuation of ODEFSEY. Patients coinfected with HIV-1 and HBV who discontinue ODEFSEY should be closely monitored with both clinical and laboratory follow-up for at least several months after stopping treatment. If appropriate, initiation of antihepatitis B therapy may be warranted, especially in patients with advanced liver disease or cirrhosis, since post treatment exacerbation of hepatitis may lead to hepatic decompensation and liver failure.

5.2 Skin and Hypersensitivity Reactions

Severe skin and hypersensitivity reactions, including cases of Drug Reaction with Eosinophilia and Systemic Symptoms (DRESS), have been reported during postmarketing experience with RPV-containing regimens. While some skin reactions were accompanied by constitutional symptoms such as fever, other skin reactions were associated with organ dysfunction, including elevations in hepatic serum biochemistries. During Phase 3 clinical trials of RPV, treatment-related rashes with at least Grade 2 severity were reported in 1% of subjects. Overall, most rashes were Grade 1 or 2 and occurred in the first four to six weeks of therapy [see Adverse Reactions (6.2)].

Discontinue ODEFSEY immediately if signs or symptoms of severe skin or hypersensitivity reactions develop, including but not limited to, severe rash or rash accompanied by fever, blisters, mucosal involvement, conjunctivitis, facial edema, angioedema, hepatitis, or eosinophilia. Clinical status including laboratory parameters should be monitored and appropriate therapy should be initiated.

5.3 Loss of Virologic Response Due to Drug Interactions

The concomitant use of ODEFSEY and other drugs may result in known or potentially significant drug interactions, some of which may lead to loss of therapeutic effect of ODEFSEY and possible development of resistance due to reduced exposure of RPV.

See Table 3 for steps to prevent or manage these possible and known significant drug interactions, including dosing recommendations [see Contraindications (4) and Drug Interactions (7)]. Consider the potential for drug interactions prior to and during ODEFSEY therapy; review concomitant medications during ODEFSEY therapy; and monitor for the adverse reactions associated with the concomitant drugs.

5.4 Prolongation of QTc Interval with Higher Than Recommended Dosages

In healthy subjects, higher than recommended doses of RPV (75 mg once daily and 300 mg once daily – 3 and 12 times the recommended dosages, respectively) have been shown to prolong the QTc interval of the electrocardiogram [see Drug Interactions (7.2) and Clinical Pharmacology (12.2)]. Consider alternatives to ODEFSEY when coadministered with a drug with a known risk of Torsade de Pointes or when administered to patients at higher risk of Torsades de Pointes.

5.5 Depressive Disorders

Depressive disorders (including depressed mood, depression, dysphoria, major depression, mood altered, negative thoughts, suicide attempt, suicidal ideation) have been reported with RPV. Promptly evaluate patients with severe depressive symptoms to assess whether the symptoms are related to ODEFSEY, and to determine whether the risks of continued therapy outweigh the benefits.

In Phase 3 trials of RPV in adult subjects (N=1368) through 96 weeks, the incidence of depressive disorders (regardless of causality, severity) reported among RPV-treated subjects (n=686) was 9%. Most events were mild or moderate in severity. In RPV-treated subjects, the incidence of Grades 3 and 4 depressive disorders (regardless of causality) was 1%, the incidence of discontinuation due to depressive disorders was 1%, and suicidal ideation and suicide attempt was reported in 4 and 2 subjects, respectively.

During the Phase 2 trial in RPV-treated pediatric subjects 12 to less than 18 years of age (N=36), the incidence of depressive disorders (regardless of causality, severity) was 19% (7/36) through 48 weeks. Most events were mild or moderate in severity. The incidence of Grade 3 and 4 depressive disorders (regardless of causality) was 6% (2/36). None of the subjects discontinued due to depressive disorders. Suicidal ideation and suicide attempt were reported in 1 subject.

5.6 Hepatotoxicity

Hepatic adverse events have been reported in patients receiving an RPV-containing regimen. Patients with underlying hepatitis B or C, or marked elevations in liver-associated tests prior to treatment, may be at increased risk for worsening or development of liver-associated test elevations with use of ODEFSEY. A few cases of hepatic toxicity have been reported in adult patients receiving a RPV-containing regimen who had no preexisting hepatic disease or other identifiable risk factors. Appropriate laboratory testing prior to initiating therapy and monitoring for hepatotoxicity during therapy with ODEFSEY is recommended in patients with underlying hepatic disease such as hepatitis B or C, or in patients with marked elevations in liver-associated tests prior to treatment initiation. Liver-associated test monitoring should also be considered for patients without preexisting hepatic dysfunction or other risk factors.

5.7 Immune Reconstitution Syndrome

Immune reconstitution syndrome has been reported in patients treated with combination antiretroviral therapy, including FTC and RPV, both components of ODEFSEY. During the initial phase of combination antiretroviral treatment, patients whose immune system responds may develop an inflammatory response to indolent or residual opportunistic infections [such as Mycobacterium avium infection, cytomegalovirus, Pneumocystis jirovecii pneumonia (PCP), or tuberculosis], which may necessitate further evaluation and treatment.

Autoimmune disorders (such as Graves' disease, polymyositis, and Guillain-Barré syndrome) have also been reported to occur in the setting of immune reconstitution, however, the time to onset is more variable, and can occur many months after initiation of treatment.

5.8 New Onset or Worsening Renal Impairment

Renal impairment, including cases of acute renal failure and Fanconi syndrome (renal tubular injury with severe hypophosphatemia), has been reported with the use of tenofovir prodrugs in both animal toxicology studies and human trials. In clinical trials of FTC+TAF with EVG+COBI, there have been no cases of Fanconi syndrome or proximal renal tubulopathy (PRT). In clinical trials of FTC+TAF with EVG+COBI in treatment-naïve subjects and in virologically-suppressed subjects switched to FTC+TAF with EVG+COBI with eGFRs greater than 50 mL per minute, renal serious adverse events or discontinuations due to renal adverse reactions were encountered in less than 1% of participants treated with FTC+TAF with EVG+COBI. In a study of virologically-suppressed subjects with baseline eGFRs between 30 and 69 mL per minute treated with FTC+TAF with EVG+COBI for a median duration of 43 weeks, FTC+TAF with EVG+COBI was permanently discontinued due to worsening renal function in two of 80 (3%) subjects with a baseline eGFR between 30 and 50 mL per minute [see Adverse Reactions (6.1)]. ODEFSEY is not recommended in patients with estimated creatinine clearance below 30 mL per minute because data in this population are insufficient.

Patients taking tenofovir prodrugs who have impaired renal function and those taking nephrotoxic agents, including nonsteroidal anti-inflammatory drugs are at increased risk of developing renal-related adverse reactions.

It is recommended that serum creatinine, serum phosphorus, estimated creatinine clearance, urine glucose and urine protein be assessed before initiating ODEFSEY therapy and during therapy in all patients as clinically appropriate. Discontinue ODEFSEY in patients who develop clinically significant decreases in renal function or evidence of Fanconi syndrome.

5.9 Lactic Acidosis/Severe Hepatomegaly with Steatosis

Lactic acidosis and severe hepatomegaly with steatosis, including fatal cases, have been reported with the use of nucleoside analogs, including emtricitabine, a component of ODEFSEY, and tenofovir DF, another prodrug of tenofovir, alone or in combination with other antiretrovirals. Treatment with ODEFSEY should be suspended in any patient who develops clinical or laboratory findings suggestive of lactic acidosis or pronounced hepatotoxicity (which may include hepatomegaly and steatosis even in the absence of marked transaminase elevations).

6 ADVERSE REACTIONS

The following adverse reactions are discussed in other sections of the labeling:

- Severe Acute Exacerbations of Hepatitis B [See Warnings and Precautions (5.1)]
- Skin and Hypersensitivity Reactions [See Warnings and Precautions (5.2)]
- Depressive Disorders [See Warnings and Precautions (5.5)]
- Hepatotoxicity [See Warnings and Precautions (5.6)]
- Immune Reconstitution Syndrome [See Warnings and Precautions (5.7)]
- New Onset or Worsening Renal Impairment [see Warnings and Precautions (5.8)]
- Lactic Acidosis/Severe Hepatomegaly with Steatosis [See Warnings and Precautions (5.9)]

6.1 Clinical Trials Experience

Because clinical trials are conducted under widely varying conditions, adverse reaction rates observed in the clinical trials of a drug (or a drug given in various combinations with other concomitant therapy) cannot be directly compared to rates in the clinical trials of another drug (or drug given in the same or different combination therapy) and may not reflect the rates observed in practice.

Adverse Reactions in Clinical Trials of ODEFSEY in Virologically-Suppressed Adult Subjects with HIV-1 Infection

The safety of ODEFSEY in virologically-suppressed adults is based on Week 48 data from two randomized, double-blinded, active-controlled clinical trials, 1160 and 1216, that enrolled 1505 adult subjects who were virologically-suppressed for at least 6 months. Both trials were designed to compare switching to ODEFSEY to maintaining efavirenz/emtricitabine/tenofovir disoproxil fumarate (EFV/FTC/TDF) or emtricitabine/rilpivirine/tenofovir disoproxil fumarate (FTC/RPV/TDF) in Trials 1160 and 1216, respectively. A total of 754 subjects received one tablet of ODEFSEY daily [see Clinical Studies (14.1)].

The most common adverse reactions (all Grades) reported in at least 2% of subjects in the ODEFSEY group across Trials 1216 and 1160 were headache and sleep disturbances (Table 1). Over 98% of the adverse reactions in the ODEFSEY group were of mild to moderate intensity. The proportion of subjects who discontinued treatment with ODEFSEY due to adverse events, regardless of severity, was 2% compared to 1% for FTC/RPV/TDF and 2% for EFV/FTC/TDF.

Table 1 Adverse Reactions [a. Frequencies of adverse reactions are based on all adverse events attributed to study drugs by the investigator.] (All Grades) Reported in ≥1% of HIV-1 Infected Virologically-Suppressed Adults in Trial 1160 or Trial 1216 (Week 48 analysis)
Adverse Reaction | Trial 1160 |  | Trial 1216
 | ODEFSEY (N=438) | EFV/FTC/TDF (N=437) [Data from Trials 1160 and 1216 do not provide an adequate basis for comparison of adverse reaction incidences between ODEFSEY and the FTC/RPV/TDF and EFV/FTC/TDF groups.] | ODEFSEY (N=316) | FTC/RPV/TDF (N=313)
Headache | 2% | 1% | 0 | 1%
Flatulence | 1% | <1% | <1% | 1%
Sleep Disturbances | 2% | 1% | 0 | <1%
Abnormal Dreams | 1% | 1% | 0 | 2%
Diarrhea | 1% | 3% | 1% | 2%
Nausea | 1% | 1% | 1% | 1%

Renal Laboratory Tests

In Trial 1216, the median baseline eGFR was104 mL per minute for subjects who switched to ODEFSEY from FTC/RPV/TDF (N=316) and the mean serum creatinine decreased by 0.02 mg per dL from baseline to Week 48.

In Trial 1160, the median baseline eGFR was 110 mL per minute for subjects who switched to ODEFSEY from EFV/FTC/TDF (N=438), and the mean serum creatinine increased by 0.1 mg per dL from baseline to Week 48.

Bone Mineral Density Effects

Changes in BMD from baseline to Week 48 were assessed by dual-energy X-ray absorptiometry (DXA) in Trials 1216 and 1160.

In Trial 1216, mean bone mineral density (BMD) increased in subjects who switched to ODEFSEY (1.61% lumbar spine, 1.04% total hip) and remained stable or decreased in subjects who remained on FTC/RPV/TDF (0.08% lumbar spine, –0.25% total hip). BMD declines of 5% or greater at the lumbar spine were experienced by 1.7% of ODEFSEY subjects and 3.0% of FTC/RPV/TDF subjects. BMD declines of 7% or greater at the femoral neck were experienced by 0% of ODEFSEY subjects and 1.2% of FTC/RPV/TDF subjects.

In Trial 1160, mean BMD increased in subjects who switched to ODEFSEY (1.65% lumbar spine, 1.28% total hip) and decreased slightly in subjects who remained on EFV/FTC/TDF (–0.05% lumbar spine, –0.13% total hip). BMD declines of 5% or greater at the lumbar spine were experienced by 2.3% of ODEFSEY subjects and 4.9% of EFV/FTC/TDF subjects. BMD declines of 7% or greater at the femoral neck were experienced by 1.4% of ODEFSEY subjects and 3.3% of EFV/FTC/TDF subjects. The long-term clinical significance of these BMD changes is not known.

Serum Lipids

Changes from baseline in total cholesterol, HDL-cholesterol, LDL-cholesterol, triglycerides, and total cholesterol to HDL ratio for Trials 1216 and 1160 are presented in Table 2.

Table 2 Lipid Values, Mean Change from Baseline Reported in Subjects Receiving ODEFSEY, FTC/RPV/TDF and EFV/FTC/TDF in Trials 1216 and 1160 at 48 Weeks
 | Trial 1216 |  |  |  | Trial 1160
 | ODEFSEY N=316 [n=235] |  | FTC/RPV/TDF N=314 [n=245] |  | ODEFSEY N=438 [n=295] |  | EFV/FTC/TDF N=437 [n=308]
 | Baseline | Week 48 | Baseline | Week 48 | Baseline | Week 48 | Baseline | Week 48
 | mg/dL | Change [The change from baseline is the mean of within-subject changes from baseline for subjects with both baseline and Week 48 values.] , [Subjects who received lipid-lowering agents during the treatment period were excluded.] | mg/dL | Change, | mg/dL | Change, | mg/dL | Change,
Total Cholesterol (fasted) | 176 | +17 | 171 | 0 | 193 | -7 | 192 | -3
HDL-Cholesterol (fasted) | 50 | +3 | 48 | 0 | 56 | -4 | 55 | -2
LDL-Cholesterol (fasted) | 111 | +13 | 108 | +1 | 118 [[n=296] for ODEFSEY group in Study 1160 for LDL-Cholesterol (fasted)] | -1 | 119 | -1
Triglycerides (fasted) | 116 | +12 | 119 | -9 | 139 | -12 | 133 | +3
Total Cholesterol to HDL Ratio | 3.7 | +0.2 | 3.8 | +0.1 | 3.7 | +0.2 | 3.8 | 0

Adverse Reactions in Clinical Trials of RPV-Containing Regimens in Treatment-Naïve Adult Subjects with HIV-1 Infection

In pooled 96-week trials of antiretroviral treatment-naïve HIV-1 infected adult subjects, the most common adverse reactions in subjects treated with RPV+FTC/TDF (N=550) (incidence greater than or equal to 2%, Grades 2−4) were headache, depressive disorders, and insomnia. The proportion of subjects who discontinued treatment with RPV+FTC/TDF due to adverse reactions, regardless of severity, was 2%. The most common adverse reactions that led to discontinuation in this treatment group were psychiatric disorders (1.6%) and rash (0.2%). Although the safety profile was similar in virologically-suppressed adults with HIV-1 infection who were switched to RPV and other antiretroviral drugs, the frequency of adverse events increased by 20% (N=317).

Adverse Reactions in Clinical Trials of FTC+TAF with EVG+COBI in Treatment-Naïve Adult Subjects with HIV-1 Infection

In pooled 48-week trials of antiretroviral treatment-naïve HIV-1 infected adult subjects, the most common adverse reaction in subjects treated with FTC+TAF with EVG+COBI (N=866) (incidence greater than or equal to 10%, all grades) was nausea (10%). In this treatment group, 0.9% of subjects discontinued FTC+TAF with EVG+COBI due to adverse event [see Clinical Studies (14)]. Antiretroviral treatment-naïve adult subjects treated with FTC+TAF with EVG+COBI experienced mean increases of 30 mg/dL of total cholesterol, 15 mg/dL of LDL cholesterol, 7 mg/dL of HDL cholesterol and 29 mg/dL of triglycerides after 48 weeks of use.

Renal Laboratory Tests

In two 48-week trials in antiretroviral treatment-naïve HIV-1 infected adults treated with FTC+TAF with EVG+COBI (N=866) with a median baseline eGFR of 115 mL per minute, mean serum creatinine increased by 0.1 mg per dL from baseline to Week 48. In a 24-week trial in adults with renal impairment (baseline eGFR 30 to 69 mL per minute) who received FTC+TAF with EVG+COBI (N=248), mean serum creatinine was 1.5 mg per dL at both baseline and Week 24.

Bone Mineral Density Effects

In the pooled analysis of two 48-week trials of antiretroviral treatment-naïve HIV-1 infected adult subjects, bone mineral density (BMD) from baseline to Week 48 was assessed by dual-energy X-ray absorptiometry (DXA). Mean BMD decreased from baseline to Week 48 by −1.30% with FTC+TAF with EVG+COBI at the lumbar spine and -0.66% at the total hip. BMD declines of 5% or greater at the lumbar spine were experienced by 10% of FTC+TAF with EVG+COBI subjects. BMD declines of 7% or greater at the femoral neck were experienced by 7% of FTC+TAF with EVG+COBI subjects. The long-term clinical significance of these BMD changes is not known.

Adverse Reactions in Clinical Trials in Pediatric Subjects with HIV-1 Infection

In an open-label 48-week trial of 36 antiretroviral treatment-naïve HIV-1 infected pediatric subjects 12 to less than 18 years old (weighing at least 32 kg) treated with 25 mg per day of RPV and other antiretrovirals, the most common adverse reactions were headache (19%), depression (19%), somnolence (14%), nausea (11%), dizziness (8%), abdominal pain (8%), vomiting (6%) and rash (6%).

In a 24-week, open-label trial of 23 antiretroviral treatment-naïve HIV-1 infected pediatric subjects aged 12 to less than 18 years old (weighing at least 35 kg) who received FTC+TAF with EVG+COBI, the safety of this combination was similar to that of adults. Among these pediatric subjects, mean BMD increased from baseline to Week 24, +1.7% at the lumbar spine and +0.8% for the total body less head. Mean changes from baseline BMD Z-scores were -0.10 for lumbar spine and -0.11 for total body less head at Week 24. Two subjects had significant (greater than 4%) lumbar spine BMD loss at Week 24.

6.2 Postmarketing Experience

The following adverse reactions have been identified during postmarketing experience in patients receiving RPV-containing regimens. Because these reactions are reported voluntarily from a population of uncertain size, it is not always possible to reliably estimate their frequency or establish a causal relationship to drug exposure.

Metabolism and Nutrition Disorders

Weight increased

Skin and Subcutaneous Tissue Disorders

Severe skin and hypersensitivity reactions including DRESS (Drug Reaction with Eosinophilia and Systemic Symptoms)

Renal and Urinary Disorders

Nephrotic syndrome

7 DRUG INTERACTIONS

7.1 Potential for Other Drugs to Affect One or More Components of ODEFSEY

Drugs that Induce or Inhibit CYP3A Enzymes

RPV is primarily metabolized by CYP3A, and drugs that induce or inhibit CYP3A may affect the clearance of RPV [see Clinical Pharmacology (12.3)]. Coadministration of RPV and drugs that induce CYP3A may result in decreased plasma concentrations of RPV and loss of virologic response and possible resistance to RPV or to the class of NNRTIs [see Contraindications (4), Warnings and Precautions (5.3), and Table 3]. These drugs are contraindicated and include:

- the anticonvulsants carbamazepine, oxcarbazepine, phenobarbital, phenytoin
- the antimycobacterials rifampin and rifapentine
- the glucocorticoid systemic dexamethasone (more than a single dose)
- St. John's wort (Hypericum perforatum)

Coadministration of RPV and drugs that inhibit CYP3A may result in increased plasma concentrations of RPV and possible adverse events.

Drugs that Induce or Inhibit P-glycoprotein

TAF, a component of ODEFSEY, is a substrate of P-gp, BCRP, OATP1B1, and OATP1B3. Drugs that strongly affect P-gp and BCRP activity may lead to changes in TAF absorption (see Table 3). Drugs that induce P-gp activity are expected to decrease the absorption of TAF, resulting in decreased plasma concentration of TAF, which may lead to loss of therapeutic effect of ODEFSEY and development of resistance. Coadministration of ODEFSEY with other drugs that inhibit P-gp and BCRP may increase the absorption and plasma concentration of TAF.

Drugs that Increase Gastric pH

Coadministration of RPV with drugs that increase gastric pH may decrease plasma concentrations of RPV and lead to loss of virologic response and possible resistance to RPV or to the class of NNRTIs. Use of RPV with proton pump inhibitors is contraindicated and use of RPV with H2-receptor antagonists requires staggered administration (see see Contraindications (4) and Table 3).

7.2 QT Prolonging Drugs

There is limited information available on the potential for a pharmacodynamic interaction between RPV and drugs that prolong the QTc interval. In a study of healthy subjects, higher than recommended doses of RPV, 75 mg once daily and 300 mg once daily (3 times and 12 times recommended daily dose in ODEFSEY) prolonged the QTc interval [see Warnings and Precautions (5.4) and Clinical Pharmacology (12.2)]. Consider alternative medications to ODEFSEY in patients taking a drug with a known risk of Torsade de Pointes.

7.3 Drugs that Affect Renal Function

Because FTC and tenofovir are primarily excreted by the kidneys by a combination of glomerular filtration and active tubular secretion, coadministration of ODEFSEY with drugs that reduce renal function or compete for active tubular secretion may increase concentrations of FTC, tenofovir, and other renally eliminated drugs and this may increase the risk of adverse reactions. Some examples of drugs that are eliminated by active tubular secretion include, but are not limited to, acyclovir, cidofovir, ganciclovir, valacyclovir, valganciclovir, aminoglycosides (e.g., gentamicin), and high-dose or multiple NSAIDs [see Warnings and Precautions (5.8)].

7.4 Established and Other Potentially Significant Drug Interactions

Table 3 provides a listing of established or potentially clinically significant drug interactions with recommended steps to prevent or manage the drug interaction (the table is not all inclusive). The drug interactions described are based on studies conducted with either ODEFSEY, the components of ODEFSEY (FTC, RPV and TAF) as individual agents, or are predicted drug interactions that may occur with ODEFSEY. For pharmacokinetic data, see Tables 7–10 [see Clinical Pharmacology (12.3)].

Table 3 Established and Other Potentially Significant [This table is not all inclusive.] Drug Interactions
Concomitant Drug Class: Drug Name | Effect on Concentration [Increase=↑; Decrease=↓; No Effect=↔] | Clinical Comment
Antacids: antacids (e.g., aluminum, magnesium hydroxide, or calcium carbonate) | ↔ RPV (antacids taken at least 2 hours before or at least 4 hours after RPV) ↓ RPV (concomitant intake) | Administer antacids at least 2 hours before or at least 4 hours after ODEFSEY.
Antimycobacterials: rifabutin | ↓ RPV [The interaction was evaluated in a clinical study. All other drug interactions shown are predicted.] ↓ TAF | Coadministration of ODEFSEY with rifabutin is not recommended.
Azole Antifungal Agents: fluconazole itraconazole ketoconazole posaconazole voriconazole | ↑ RPV, [This interaction study has been performed with a dose higher than the recommended dose for RPV. The dosing recommendation is applicable to the recommended dose of RPV 25 mg once daily.] ↑ TAF ↓ ketoconazole, | No dosage adjustment is required when ODEFSEY is coadministered with azole antifungal agents. Clinically monitor for breakthrough fungal infections when azole antifungals are coadministered with ODEFSEY.
H2-Receptor Antagonists: cimetidine famotidine nizatidine ranitidine | ↔ RPV, (famotidine taken 12 hours before RPV or 4 hours after RPV) ↓ RPV, (famotidine taken 2 hours before RPV) | Administer H2-receptor antagonists at least 12 hours before or at least 4 hours after ODEFSEY.
Macrolide or Ketolide Antibiotics: clarithromycin erythromycin telithromycin | ↑ RPV ↔ clarithromycin ↔ erythromycin ↔ telithromycin | Where possible, alternatives such as azithromycin should be considered.
Narcotic Analgesics: methadone | ↓ R(–) methadone ↓ S(+) methadone ↔ RPV ↔ methadone (when used with tenofovir) | No dosage adjustments are required when initiating coadministration of methadone with ODEFSEY. However, clinical monitoring is recommended, as methadone maintenance therapy may need to be adjusted in some patients.

7.5 Drugs Without Clinically Significant Interactions with ODEFSEY

Based on drug interaction studies conducted with the fixed dose combination or components of ODEFSEY, no clinically significant drug interactions have been either observed or expected when ODEFSEY is combined with the following drugs: acetaminophen, atorvastatin, buprenorphine, chlorzoxazone, digoxin, ethinyl estradiol, ledipasvir, lorazepam, metformin, midazolam, naloxone, norbuprenorphine, norethindrone, norgestimate/ethinyl estradiol, sildenafil, simeprevir, sofosbuvir, and velpatasvir.

8 USE IN SPECIFIC POPULATIONS

8.1 Pregnancy

Pregnancy Exposure Registry

There is a pregnancy exposure registry that monitors pregnancy outcomes in women exposed to ODEFSEY during pregnancy. Healthcare providers are encouraged to register patients by calling the Antiretroviral Pregnancy Registry (APR) at 1-800-258-4263.

Risk Summary

There are insufficient human data on the use of ODEFSEY during pregnancy to inform a drug-associated risk of birth defects and miscarriage. Tenofovir alafenamide (TAF) use in women during pregnancy have not been evaluated; however, emtricitabine (FTC) and rilpivirine (RPV) use during pregnancy has been evaluated in a limited number of women reported to the APR. Available data from the APR show no difference in the risk of overall major birth defects for FTC and RPV compared with the background rate for major birth defects of 2.7% in a US reference population of the Metropolitan Atlanta Congenital Defects Program (MACDP). The rate of miscarriage is not reported in the APR. The estimated background rate of miscarriage in the clinically recognized pregnancies in the U.S. general population is 15–20%. Methodological limitations of the APR include the use of MACDP as the external comparator group. The MACDP population is not disease-specific, evaluates women and infants from a limited geographic area, and does not include outcomes for births that occurred at <20 weeks gestation.

In animal studies, no adverse developmental effects were observed when the components of ODEFSEY were administered separately during the period of organogenesis at exposures up to 60 and 108 times (mice and rabbits, respectively; FTC), 15 and 70 times (rats and rabbits, respectively; RPV) and equal to and 53 times (rats and rabbits, respectively; TAF) the exposure at the recommended daily dose of these components in ODEFSEY [see Data (8.1)]. Likewise, no adverse developmental effects were seen when FTC was administered to mice and RPV was administered to rats through lactation at exposures up to approximately 60 and 63 times, respectively, the exposure at the recommended daily dose of these components in ODEFSEY. No adverse effects were observed in the offspring when TDF was administered through lactation at tenofovir exposures of approximately 14 times the exposure at the recommended daily dosage of ODEFSEY.

Data

Human Data

Emtricitabine: Based on prospective reports to the APR of 3406 exposures to FTC-containing regimens during pregnancy (including 2326 exposed in the first trimester and 1080 exposed in the second/third trimester), there was no difference between FTC and overall birth defects compared with the background birth defect rate of 2.7% in the U.S. reference population of the MACDP. The prevalence of birth defects in live births was 2.3% (95% CI: 1.7% to 3.0%) with first trimester exposure to FTC-containing regimens and 2.0% (95% CI: 1.3% to 3.1%) with second/third trimester exposure to FTC-containing regimens.

Rilpivirine: Based on prospective reports to the APR of 326 live births following exposures to RPV-containing regimens during pregnancy (including 202 exposed in the first trimester and 124 exposed in the second/third trimester), there was no difference in the rate of overall birth defects for RPV compared with the background rate of 2.7% for major birth defects in the U.S. reference population of the MACDP. The prevalence of birth defects in live births was 0.5% (95% CI: 0.0% to 2.7%) with first trimester exposure to RPV-containing regimens and 0.8% (95% CI: 0.0% to 4.4%) with second/third trimester exposure to RPV-containing regimens.

Animal Data

Emtricitabine: FTC was administered orally to pregnant mice (250, 500, or 1000 mg/kg/day) and rabbits (100, 300, or 1000 mg/kg/day) through organogenesis (on gestation days 6 through 15, and 7 through 19, respectively). No significant toxicological effects were observed in embryo-fetal toxicity studies performed with FTC in mice at exposures (AUC) approximately 60 times higher and in rabbits at approximately 108 times higher than human exposures at the recommended daily dose. In a pre/postnatal development study with FTC, mice were administered doses up to 1000 mg/kg/day; no significant adverse effects directly related to drug were observed in the offspring exposed daily from before birth (in utero) through sexual maturity at daily exposures (AUC) of approximately 60-fold higher than human exposures at the recommended daily dose.

Rilpivirine: RPV was administered orally to pregnant rats (40, 120, or 400 mg/kg/day) and rabbits (5, 10, or 20 mg/kg/day) through organogenesis (on gestation days 6 through 17, and 6 through 19, respectively). No significant toxicological effects were observed in embryo-fetal toxicity studies performed with RPV in rats and rabbits at exposures 15 (rats) and 70 (rabbits) times higher than the exposure in humans at the recommended dose of 25 mg once daily. In a pre/postnatal development study with RPV, where rats were administered up to 400 mg/kg/day through lactation, no significant adverse effects directly related to drug were noted in the offspring.

Tenofovir Alafenamide: TAF was administered orally to pregnant rats (25, 100, or 250 mg/kg/day) and rabbits (10, 30, or 100 mg/kg/day) through organogenesis (on gestation days 6 through 17, and 7 through 20, respectively). No adverse embryo-fetal effects were observed in rats and rabbits at TAF exposures similar to (rats) and approximately 53 (rabbits) times higher than the exposure in humans at the recommended daily dose of ODEFSEY. TAF is rapidly converted to tenofovir; the observed tenofovir exposure in rats and rabbits were 59 (rats) and 93 (rabbits) times higher than human tenofovir exposures at the recommended daily doses. Since TAF is rapidly converted to tenofovir and a lower tenofovir exposure in rats and mice was observed after TAF administration compared to tenofovir disoproxil fumarate (TDF, another prodrug for tenofovir) administration, a pre/postnatal development study in rats was conducted only with TDF. Doses up to 600 mg/kg/day were administered through lactation, no adverse effects were observed in the offspring on gestation day 7 [and lactation day 20] at tenofovir exposures of approximately 14 [21] times higher than the exposures in humans at the recommended daily dose of ODEFSEY.

8.2 Lactation

Risk Summary

The Centers for Disease Control and Prevention recommend that HIV-infected mothers not breastfeed their infants, to avoid risking postnatal transmission of HIV.

Based on published data, FTC has been shown to be present in human breast milk; it is unknown if RPV and TAF are present in human breast milk. RPV is present in rat milk and tenofovir has been shown to be present in the milk of lactating rats and rhesus monkeys after administration of TDF [see Data]. It is unknown if TAF is present in animal milk.

It is not known if ODEFSEY affects milk production or has effects on the breastfed infant. Because of the potential for (1) HIV transmission (in HIV-negative infants), (2) developing viral resistance (in HIV-positive infants), and (3) adverse reactions in a breastfed infant similar to those seen in adults, instruct mothers not to breastfeed if they are receiving ODEFSEY.

Data

Animal Data

Rilpivirine: In animals, no studies have been conducted to assess the excretion of rilpivirine directly; however RPV was measured in rat pups which were exposed through the milk of treated dams (dosed up to 400 mg/kg/day).

Tenofovir Alafenamide: Studies in rats and monkeys have demonstrated that tenofovir is secreted in milk. Tenofovir was excreted into the milk of lactating rats following oral administration of TDF (up to 600 mg/kg/day) at up to approximately 24% of the median plasma concentration in the highest dosed animals at lactation day 11 [see Data (8.1)]. Tenofovir was excreted into the milk of lactating monkeys, following a single subcutaneous (30 mg/kg) dose of tenofovir, at concentrations up to approximately 4% of plasma concentration resulting in exposure (AUC) of approximately 20% of plasma exposure.

8.4 Pediatric Use

The efficacy and safety of ODEFSEY as a complete regimen for the treatment of HIV-1 infection was established in pediatric patients 12 years of age and older with body weight greater than or equal to 35 kg [see Dosage and Administration (2.2)]. Use of ODEFSEY in this age group is supported by adequate and well-controlled studies of RPV+FTC+TDF in adults with HIV-1 infection, adequate and well-controlled studies of FTC+TAF with EVG+COBI in adults with HIV-1 infection, and by the following pediatric studies [see Clinical Studies (14)]:

- 48-week open-label trial of 36 antiretroviral treatment-naïve HIV-1 infected pediatric subjects 12 to less than 18 years old weighing at least 32 kg treated with 25 mg per day of RPV and other antiretrovirals. The safety and efficacy of RPV and other antiretrovirals was similar to that of antiretroviral treatment-naïve HIV-1 infected adults on this regimen.
- 24-week open-label trial of 23 antiretroviral treatment-naïve HIV-1 infected pediatric subjects 12 to less than 18 years old (weighing at least 35 kg) treated with FTC+TAF with EVG+COBI. The safety and efficacy of FTC+TAF with EVG+COBI was similar to that of antiretroviral treatment-naïve HIV-1 infected adults on this regimen.

Because it is a fixed-dose combination tablet, the dose of ODEFSEY cannot be adjusted for patients of lower age and weight. The safety and efficacy of ODEFSEY have not been established in pediatric patients less than 12 years of age or weighing less than 35 kg [see Clinical Pharmacology (12.3)].

8.5 Geriatric Use

In clinical trials, 80 of the 97 subjects enrolled aged 65 years and over received FTC+TAF with EVG+COBI. No differences in safety or efficacy have been observed between elderly subjects and those between 12 and less than 65 years of age. Clinical trials of RPV did not include sufficient numbers of subjects aged 65 years and over to determine whether they respond differently from younger subjects [see Clinical Pharmacology (12.3)].

8.6 Renal Impairment

ODEFSEY is not recommended in patients with severe renal impairment (estimated creatinine clearance below 30 mL per minute). No dosage adjustment of ODEFSEY is recommended in patients with estimated creatinine clearance greater than or equal to 30 mL per minute [see Dosage and Administration (2.2), Clinical Pharmacology (12.3) and Clinical Studies (14)].

8.7 Hepatic Impairment

No dosage adjustment of ODEFSEY is recommended in patients with mild (Child-Pugh Class A) or moderate (Child-Pugh Class B) hepatic impairment. ODEFSEY has not been studied in patients with severe hepatic impairment (Child-Pugh Class C) [see Clinical Pharmacology (12.3)].

10 OVERDOSAGE

No data are available on overdose of ODEFSEY in patients. If overdose occurs, monitor the patient for evidence of toxicity. Treatment of overdose with ODEFSEY consists of general supportive measures including monitoring of vital signs and ECG (QT interval) as well as observation of the clinical status of the patient.

Emtricitabine (FTC): Limited clinical experience is available at doses higher than the recommended dosage of FTC in ODEFSEY. In one clinical pharmacology study, single doses of FTC 1200 mg (6 times the dose in ODEFSEY) were administered to 11 subjects. No severe adverse reactions were reported. The effects of higher doses are not known.

Hemodialysis treatment removes approximately 30% of the FTC dose over a 3-hour dialysis period starting within 1.5 hours of FTC dosing (blood flow rate of 400 mL per minute and a dialysate flow rate of 600 mL per minute). It is not known whether FTC can be removed by peritoneal dialysis.

Rilpivirine (RPV): Human experience of overdose with RPV is limited. There is no specific antidote for overdose with RPV. Since RPV is highly bound to plasma protein, dialysis is unlikely to result in significant removal of RPV.

Administration of activated charcoal may be used to aid in removal of unabsorbed active substance.

Tenofovir Alafenamide (TAF): Limited clinical experience is available at doses higher than the recommended dosage of TAF in ODEFSEY. A single dose of 125 mg TAF (5 times the dose of TAF in ODEFSEY) was administered to 48 healthy subjects; no serious adverse reactions were reported. The effects of higher doses are unknown. Tenofovir is efficiently removed by hemodialysis with an extraction coefficient of approximately 54%.

11 DESCRIPTION

ODEFSEY (emtricitabine, rilpivirine, and tenofovir alafenamide) is a fixed-dose combination tablet containing emtricitabine (FTC), rilpivirine (RPV), and tenofovir alafenamide (TAF) for oral administration.

- FTC, a synthetic nucleoside analog of cytidine, is an HIV-1 nucleoside analog reverse transcriptase inhibitor (HIV-1 NRTI).
- RPV is an HIV-1 non-nucleoside reverse transcriptase inhibitor (NNRTI).
- TAF, an HIV-1 NRTI, is converted in vivo to tenofovir, an acyclic nucleoside phosphonate (nucleotide) analog of adenosine 5′-monophosphate.

Each tablet contains 200 mg of FTC, 25 mg of RPV (equivalent to 27.5 of rilpivirine hydrochloride) and 25 mg of TAF (equivalent to 28 mg of tenofovir alafenamide fumarate) and the following inactive ingredients: croscarmellose sodium, lactose monohydrate, magnesium stearate, microcrystalline cellulose, polysorbate 20, and povidone. The tablets are film-coated with a coating material containing iron oxide black, polyethylene glycol, polyvinyl alcohol, talc, and titanium dioxide.

Emtricitabine: The chemical name of FTC is 4-amino-5-fluoro-1-(2R-hydroxymethyl-1,3-oxathiolan-5S-yl)-(1H)-pyrimidin-2-one. FTC is the (-)enantiomer of a thio analog of cytidine, which differs from other cytidine analogs in that it has a fluorine in the 5 position.

FTC has a molecular formula of C8H10FN3O3S and a molecular weight of 247.24 and has the following structural formula:

FTC is a white to off-white powder with a solubility of approximately 112 mg per mL in water at 25 °C.

Rilpivirine: The chemical name of rilpivirine hydrochloride drug substance is 4-[[4-[[4-[(E)-2-cyanoethenyl]-2,6-dimethylphenyl]amino]-2-pyrimidinyl]amino]benzonitrile monohydrochloride. Its molecular formula is C22H18N6 ∙ HCl and its molecular weight is 402.88. Rilpivirine hydrochloride has the following structural formula:

Rilpivirine hydrochloride is a white to almost white powder. Rilpivirine hydrochloride is practically insoluble in water over a wide pH range.

Tenofovir Alafenamide: The chemical name of tenofovir alafenamide fumarate drug substance is L-alanine, N-[(S)-[[(1R)-2-(6-amino-9H-purin-9-yl)-1-methylethoxy]methyl]phenoxyphosphinyl]-, 1-methylethyl ester, (2E)-2-butenedioate (2:1).

Tenofovir alafenamide fumarate has an empirical formula of C21H29O5N6P∙½(C4H4O4) and a formula weight of 534.50 and has the following structural formula:

Tenofovir alafenamide fumarate is a white to off-white or tan powder with a solubility of 4.7 mg per mL in water at 20 °C.

12 CLINICAL PHARMACOLOGY

12.1 Mechanism of Action

ODEFSEY is a fixed dose combination of antiretroviral drugs emtricitabine, rilpivirine, and tenofovir alafenamide [see Microbiology (12.4)].

12.2 Pharmacodynamics

Cardiac Electrophysiology

When higher than recommended RPV doses of 75 mg (3 times the recommended dosage in ODEFSEY) once daily and 300 mg (12 times the recommended dosage in ODEFSEY) once daily were studied in healthy adults, the maximum mean time-matched (95% upper confidence bound) differences in QTcF interval from placebo after baseline correction were 10.7 (15.3) and 23.3 (28.4) milliseconds, respectively. Steady-state administration of RPV 75 mg once daily and 300 mg once daily resulted in a mean steady-state Cmax approximately 2.6 times and 6.7 times, respectively, higher than the mean Cmax observed with the recommended 25 mg once daily dose of RPV [see Warnings and Precautions (5.4)].

The effect of RPV at the recommended dose of 25 mg once daily on the QTcF interval was evaluated in a randomized, placebo-, and active- (moxifloxacin 400 mg once daily) controlled crossover study in 60 healthy adults, with 13 measurements over 24 hours at steady state. The maximum mean time-matched (95% upper confidence bound) differences in QTcF interval from placebo after baseline correction was 2 (5) milliseconds (i.e., below the threshold of clinical concern).

In a thorough QT/QTc study in 48 healthy subjects, TAF at the recommended dose and at a dose approximately 5 times the recommended dose, did not affect the QT/QTc interval and did not prolong the PR interval.

The effect of FTC on the QT interval is not known.

12.3 Pharmacokinetics

Absorption, Distribution, Metabolism, and Excretion

The pharmacokinetic properties of the components of ODEFSEY are provided in Table 4. The multiple dose pharmacokinetic parameters of FTC, RPV and TAF and its metabolite tenofovir are provided in Table 5.

Table 4 Pharmacokinetic Properties of the Components of ODEFSEY
 | Rilpivirine | Emtricitabine | Tenofovir Alafenamide
Absorption
Tmax (h) | 4 | 3 | 1
Effect of moderate fat meal (relative to fasting) [Values refer to geometric mean ratio [fed/ fasted] in PK parameters and (90% confidence interval). High-calorie/high-fat meal = ~800 kcal, 50% fat. Moderate-fat meal = ~600 kcal, 27% fat.] | AUC Ratio = 1.13 (1.03, 1.23) | AUC Ratio = 0.91 (0.89, 0.93) | AUC Ratio = 1.45 (1.33, 1.58)
Effect of high fat meal (relative to fasting) | AUC Ratio = 1.72 (1.49, 1.99) | AUC Ratio = 0.88 (0.85, 0.90) | AUC Ratio = 1.53 (1.39, 1.69)
Distribution
% Bound to human plasma proteins | ~99 | <4 | ~80
Source of protein binding data | In vitro | In vitro | Ex vivo
Blood-to-plasma ratio | 0.7 | 0.6 | 1.0
Metabolism
Metabolism | CYP3A | Not significantly metabolized | Cathepsin A [In vivo, TAF is hydrolyzed within cells to form tenofovir (major metabolite), which is phosphorylated to the active metabolite, tenofovir diphosphate. In vitro studies have shown that TAF is metabolized to tenofovir by cathepsin A in PBMCs and macrophages; and by CES1 in hepatocytes. Upon coadministration with the moderate CYP3A inducer probe efavirenz, TAF exposure was unaffected.] (PBMCs) CES1 (hepatocytes) CYP3A (minimal)
Elimination
Major route of elimination | Metabolism | Glomerular filtration and active tubular secretion | Metabolism (>80% of oral dose)
t1/2 (h) [t1/2 values refer to median terminal plasma half-life. Note that the pharmacologically active metabolite, tenofovir diphosphate, has a half-life of 150–180 hours within PBMCs.] | 50 | 10 | 0.51
% Of dose excreted in urine [Dosing in mass balance studies: FTC (single dose administration of [^14C] emtricitabine after multiple dosing of emtricitabine for ten days); TAF (single dose administration of [^14C] tenofovir alafenamide).] | 6 | 70 | <1
% Of dose excreted in feces | 85 | 13.7 | 31.7
PBMCs = peripheral blood mononuclear cells; CES1 = carboxylesterase 1.

Table 5 Multiple Dose Pharmacokinetic Parameters of Emtricitabine, Rilpivirine, Tenofovir Alafenamide and its Metabolite Tenofovir Following Oral Administration with a Meal in HIV-Infected Adults
Parameter Mean (CV%) | Emtricitabine [From Intensive PK analysis in a phase 2 trial in HIV infected adults treated with FTC+TAF with EVG+COBI (n=19).] | Rilpivirine [From Population PK analysis in a trial of treatment-naïve adults with HIV-1 infection treated with RPV (n=679).] | Tenofovir Alafenamide [From Population PK analysis in two trials of treatment-naïve adults with HIV-1 infection treated within EVG+COBI+FTC+TAF (n=539).] | Tenofovir [From Population PK analysis in two trials of treatment-naïve adults with HIV-1 infection treated with EVG+COBI+FTC+TAF (n=841).]
Cmax (microgram per mL) | 2.1 (20.2) | NA | 0.16 (51.1) | 0.02 (26.1)
AUCtau (microgram∙hour per mL) | 11.7 (16.6) | 2.2 (38.1) | 0.21 (71.8) | 0.29 (27.4)
Ctrough (microgram per mL) | 0.10 (46.7) | 0.08 (44.3) | NA | 0.01 (28.5)
CV = Coefficient of Variation; NA = Not Applicable

Specific Populations

Patients with Renal Impairment

Rilpivirine: Population pharmacokinetic analysis indicated that RPV exposure was similar in HIV-1 infected subjects with eGFR 60 to 89 mL per minute by Cockcroft-Gault method relative to HIV-1 infected subjects with normal renal function. There is limited or no information regarding the pharmacokinetics of RPV in patients with moderate or severe renal impairment or in patients with end-stage renal disease [see Use in Specific Populations (8.6)].

Tenofovir Alafenamide: The pharmacokinetics of FTC+TAF with EVG+COBI in HIV-1 infected subjects with renal impairment (eGFR 30 to 69 mL per minute by Cockcroft-Gault method) were evaluated within a subset of virologically-suppressed subjects in an open-label trial (Table 6).

Table 6 Pharmacokinetics of the FTC, TAF, and a Metabolite of TAF (Tenofovir) in HIV-Infected Adults with Renal Impairment as Compared to Subjects with Normal Renal Function
 | AUCtau (microgram-hour per mL) Mean (CV%)
Creatinine Clearance | ≥90 mL per minute (N=18) [From a phase 2 trial in HIV-infected adults with normal renal function treated with FTC+TAF with EVG+COBI.] | 60–89 mL per minute (N=11) [These subjects had an eGFR ranging from 60 to 69 mL per minute.] | 30–59 mL per minute (N=18)
Emtricitabine | 11.4 (11.9) | 17.6 (18.2) | 23.0 (23.6)
Tenofovir Alafenamide [AUClast] | 0.23 (47.2) | 0.24 (45.6) | 0.26 (58.8)
Tenofovir | 0.32 (14.9) | 0.46 (31.5) | 0.61 (28.4)

Patients with Hepatic Impairment

Emtricitabine: The pharmacokinetics of FTC have not been studied in subjects with hepatic impairment; however, FTC is not significantly metabolized by liver enzymes, so the impact of hepatic impairment should be limited.

Rilpivirine: In a study comparing 8 subjects with mild hepatic impairment (Child-Pugh score A) to 8 matched controls and 8 subjects with moderate hepatic impairment (Child-Pugh score B) to 8 matched controls, the multiple-dose exposure of RPV was 47% higher in subjects with mild hepatic impairment and 5% higher in subjects with moderate hepatic impairment [see Use in Specific Populations (8.7)].

Tenofovir Alafenamide: Clinically relevant changes in the pharmacokinetics of tenofovir alafenamide or its metabolite tenofovir were not observed in subjects with mild, moderate, (Child-Pugh A and B) or severe hepatic impairment (Child-Pugh C) [see Use in Specific Populations (8.7)].

Hepatitis B and/or Hepatitis C Virus Coinfection

The pharmacokinetics of FTC and TAF have not been fully evaluated in subjects coinfected with hepatitis B and/or C virus. Population pharmacokinetic analysis indicated that hepatitis B and/or C virus coinfection had no clinically relevant effect on the exposure of RPV.

Pediatric Patients

Exposures of TAF in 24 pediatric subjects with HIV-1 infection aged 12 to less than 18 years who received FTC+TAF with EVG+COBI were decreased (23% for TAF AUC) compared to exposures achieved in treatment-naïve adults following administration of FTC+TAF with EVG+COBI. These exposure differences are not thought to be clinically significant based on exposure-response relationships. FTC exposures were similar in adolescents compared to treatment-naïve adults. The PK of RPV in antiretroviral HIV-1-infected pediatric subjects 12 to less than 18 years of age who received RPV 25 mg once daily were comparable to those in HIV-1 infected adults. As in adults, there was no impact of body weight on RPV PK in pediatric subjects [see Use In Specific Populations (8.4)].

Geriatric Patients

The pharmacokinetics of FTC and TAF have not been fully evaluated in the elderly (65 years of age and older). Population pharmacokinetics analysis of HIV-infected subjects in Phase 2 and Phase 3 trials of FTC+TAF with EVG+COBI showed that age did not have a clinically relevant effect on exposures of TAF up to 75 years of age.

The pharmacokinetics of RPV have not been fully evaluated in the elderly (65 years of age and older) [see Use in Specific Populations (8.5)].

Race

Based on population pharmacokinetic analyses, no dosage adjustment is recommended based on race.

Gender

Based on population pharmacokinetic analyses, no dosage adjustment is recommended based on gender.

Drug Interaction Studies

Rilpivirine: RPV is primarily metabolized by CYP3A, and drugs that induce or inhibit CYP3A may thus affect the clearance of RPV.

RPV at a dose of 25 mg once daily is not likely to have a clinically relevant effect on the exposure of medicinal products metabolized by CYP enzymes.

TAF is not an inhibitor of CYP1A2, CYP2B6, CYP2C8, CYP2C9, CYP2C19, CYP2D6, or UGT1A1. TAF is a weak inhibitor of CYP3A in vitro. TAF is not an inhibitor or inducer of CYP3A in vivo.

The drug interaction studies described in Tables 7–10 were conducted with ODEFSEY (FTC/RPV/TAF) or the components of ODEFSEY (FTC, RPV, or TAF) administered individually.

The effects of coadministered drugs on the exposures of RPV and TAF are shown in Tables 7 and 8, respectively. The effects of RPV and TAF on the exposure of coadministered drugs are shown in Tables 9 and 10, respectively. For information regarding clinical recommendations, see Drug Interactions (7).

Table 7 Changes in Pharmacokinetic Parameters for RPV in the Presence of Coadministered Drugs in Healthy Subjects
Coadministered Drug | Dose/Schedule |  | N | Mean Ratio of RPV Pharmacokinetic Parameters With/Without Coadministered Drug (90% CI); No Effect = 1.00
Coadministered Drug | Coadministered Drug (mg) | RPV (mg) | N | Cmax | AUC | Cmin
Acetaminophen | 500 single dose | 150 once daily [25 mg, 75 mg, and 150 mg of RPV is 1, 3, and 6 times the recommended dose of RPV in ODEFSEY, respectively.] | 16 | 1.09 (1.01, 1.18) | 1.16 (1.10, 1.22) | 1.26 (1.16, 1.38)
Atorvastatin | 40 once daily | 150 once daily | 16 | 0.91 (0.79, 1.06) | 0.90 (0.81, 0.99) | 0.90 (0.84, 0.96)
Chlorzoxazone | 500 single dose taken 2 hours after RPV | 150 once daily | 16 | 1.17 (1.08, 1.27) | 1.25 (1.16, 1.35) | 1.18 (1.09, 1.28)
Ethinylestradiol/Norethindrone | 0.035 once daily /1 mg once daily | 25 once daily | 15 | ↔ [Comparison based on historic controls.] | ↔ | ↔
Famotidine | 40 single dose taken 12 hours before RPV | 150 single dose | 24 | 0.99 (0.84, 1.16) | 0.91 (0.78, 1.07) | NA
Famotidine | 40 single dose taken 2 hours before RPV | 150 single dose | 23 | 0.15 (0.12, 0.19) | 0.24 (0.20, 0.28) | NA
Famotidine | 40 single dose taken 4 hours after RPV | 150 single dose | 24 | 1.21 (1.06, 1.39) | 1.13 (1.01, 1.27) | NA
Ketoconazole | 400 once daily | 150 once daily | 15 | 1.30 (1.13, 1.48) | 1.49 (1.31, 1.70) | 1.76 (1.57, 1.97)
Methadone | 60–100 once daily, individualized dose | 25 once daily | 12 | ↔ | ↔ | ↔
Ledipasvir/Sofosbuvir [Study conducted with ODEFSEY (FTC/RPV/TAF).] | 90/400 once daily | 25 once daily | 42 | 0.97 (0.92, 1.02) | 0.95 (0.91, 0.98) | 0.93 (0.89, 0.97)
Omeprazole | 20 once daily | 25 single dose | 15 | 0.30 (0.24, 0.38) | 0.35 (0.28, 0.44) | NA
Rifabutin | 300 once daily | 25 once daily | 18 | 0.69 (0.62, 0.76) | 0.58 (0.52, 0.65) | 0.52 (0.46, 0.59)
Rifampin | 600 once daily | 150 once daily | 16 | 0.31 (0.27, 0.36) | 0.20 (0.18, 0.23) | 0.11 (0.10, 0.13)
Simeprevir | 25 once daily | 150 once daily | 23 | 1.04 (0.95, 1.30) | 1.12 (1.05, 1.19) | 1.25 (1.16, 1.35)
Sildenafil | 50 single dose | 75 once daily | 16 | 0.92 (0.85, 0.99) | 0.98 (0.92, 1.05) | 1.04 (0.98, 1.09)
Sofosbuvir/ velpatasvir | 400/100 once daily | 10 once daily [Study conducted with FTC/RPV/TDF.] | 24 | 0.93 (0.88,0.98) | 0.95 (0.90, 1.00) | 0.96 (0.90,1.03)
CI=Confidence Interval; N=maximum number of subjects with data; NA=Not Available; ↔=no change

Table 8 Changes in Pharmacokinetic Parameters for TAF in the Presence of the Coadministered Drug [All interaction studies conducted in healthy volunteers.] in Healthy Subjects
Coadministered Drug | Dose of Coadministered Drug (mg) | TAF (mg) | N | Mean Ratio of Tenofovir Alafenamide Pharmacokinetic Parameters (90% CI); No Effect = 1.00
Coadministered Drug | Dose of Coadministered Drug (mg) | TAF (mg) | N | Cmax | AUC | Cmin
Cobicistat [Increases TAF exposure via inhibition of intestinal P-glycoprotein.] | 150 once daily | 8 once daily | 12 | 2.83 (2.20, 3.65) | 2.65 (2.29, 3.07) | NC
Ledipasvir/Sofosbuvir [Study conducted with ODEFSEY (FTC/RPV/TAF).] | 90/400 once daily | 25 once daily | 42 | 1.03 (0.94, 1.14) | 1.32 (1.25, 1.40) | NC
CI=Confidence Interval; N=maximum number of subjects with data; NC=Not Calculated

Table 9 Changes in Pharmacokinetic Parameters for Coadministered Drugs in the Presence of RPV in Healthy Subjects
Coadministered Drug | Dose/Schedule |  | N | Mean Ratio of Coadministered Drug Pharmacokinetic Parameters With/Without RPV (90% CI); No Effect = 1.00
Coadministered Drug | Coadministered Drug (mg) | RPV (mg) | N | Cmax | AUC | Cmin
Acetaminophen | 500 single dose | 150 once daily [25 mg, 75 mg, and 150 mg of RPV is 1, 3, and 6 times the recommended dose of RPV in ODEFSEY, respectively.] | 16 | 0.97 (0.86, 1.10) | 0.92 (0.85, 0.99) | NA
Atorvastatin | 40 once daily | 150 once daily | 16 | 1.35 (1.08, 1.68) | 1.04 (0.97, 1.12) | 0.85 (0.69, 1.03)
2-hydroxy-atorvastatin | 40 once daily | 150 once daily | 16 | 1.58 (1.33, 1.87) | 1.39 (1.29, 1.50) | 1.32 (1.10, 1.58)
4-hydroxy-atorvastatin | 40 once daily | 150 once daily | 16 | 1.28 (1.15, 1.43) | 1.23 (1.13, 1.33) | NA
Chlorzoxazone | 500 single dose taken 2 hours after RPV | 150 once daily | 16 | 0.98 (0.85, 1.13) | 1.03 (0.95, 1.13) | NA
Digoxin | 0.5 single dose | 25 once daily | 22 | 1.06 (0.97, 1.17) | 0.98 (0.93, 1.04) [AUC(0–last)] | NA
Ethinylestradiol | 0.035 once daily | 25 once daily | 17 | 1.17 (1.06, 1.30) | 1.14 (1.10, 1.19) | 1.09 (1.03, 1.16)
Norethindrone | 1 mg once daily | 25 once daily | 17 | 0.94 (0.83, 1.06) | 0.89 (0.84, 0.94) | 0.99 (0.90, 1.08)
Ketoconazole | 400 once daily | 150 once daily | 14 | 0.85 (0.80, 0.90) | 0.76 (0.70, 0.82) | 0.34 (0.25, 0.46)
Ledipasvir | 90 once daily | 25 once daily [Study conducted with ODEFSEY (FTC/RPV/TAF).] | 41 | 1.01 (0.97, 1.05) | 1.02 (0.97, 1.06) | 1.02 (0.98, 1.07)
Sofosbuvir | 400 once daily | 25 once daily | 41 | 0.96 (0.89, 1.04) | 1.05 (1.01, 1.09) | NA
GS-331007 [The predominant circulating nucleoside metabolite of sofosbuvir.] | 400 once daily | 25 once daily | 41 | 1.08 (1.05, 1.11) | 1.08 (1.06, 1.10) | 1.10 (1.07, 1.12)
R(-) methadone | 60–100 once daily, individualized dose | 25 once daily | 13 | 0.86 (0.78, 0.95) | 0.84 (0.74, 0.95) | 0.78 (0.67, 0.91)
S(+) methadone | 60–100 once daily, individualized dose | 25 once daily | 13 | 0.87 (0.78, 0.97) | 0.84 (0.74, 0.96) | 0.79 (0.67, 0.92)
Metformin | 850 single dose | 25 once daily | 20 | 1.02 (0.95, 1.10) | 0.97 (0.90,1.06) [N (maximum number of subjects with data for AUC(0–∞)=15)] | NA
Rifampin | 600 once daily | 150 once daily | 16 | 1.02 (0.93, 1.12) | 0.99 (0.92, 1.07) | NA
25-desacetylrifampin | 600 once daily | 150 once daily | 16 | 1.00 (0.87, 1.15) | 0.91 (0.77, 1.07) | NA
Simeprevir | 150 once daily | 25 once daily | 21 | 1.10 (0.97, 1.26) | 1.06 (0.94, 1.19) | 0.96 (0.83, 1.11)
Sildenafil | 50 single dose | 75 once daily | 16 | 0.93 (0.80, 1.08) | 0.97 (0.87, 1.08) | NA
N-desmethyl-sildenafil | 50 single dose | 75 once daily | 16 | 0.90 (0.80, 1.02) | 0.92 (0.85, 0.99) | NA
Sofosbuvir | 400 once daily | 25 once daily [Study conducted with FTC/RPV/TDF.] | 24 | 1.09 (0.95, 1.25) | 1.16 (1.10, 1.24) | NA
GS-331007 | 400 once daily | 25 once daily [Study conducted with FTC/RPV/TDF.] | 24 | 0.96 (0.90, 1.01) | 1.04 (1.00, 1.07) | 1.12 (1.07, 1.17)
Velpatasvir | 100 once daily | 25 once daily | 24 | 0.96 (0.85, 1.10) | 0.99 (0.88, 1.11) | 1.02 (0.91, 1.15)
CI=Confidence Interval; N=maximum number of subjects with data; NA=Not Available

Table 10 Changes in Pharmacokinetic Parameters for Coadministered Drug in the Presence of TAF in Healthy Subjects
Coadministered Drug | Dose of Coadministered Drug (mg) | TAF (mg) | N | Mean Ratio of Coadministered Drug Pharmacokinetic Parameters (90% CI); No Effect = 1.00
Coadministered Drug | Dose of Coadministered Drug (mg) | TAF (mg) | N | Cmax | AUC | Cmin
Midazolam [A sensitive CYP3A4 substrate.] | 2.5 single dose, orally | 25 once daily | 18 | 1.02 (0.92, 1.13) | 1.13 (1.04, 1.23) | NC
Midazolam [A sensitive CYP3A4 substrate.] | 1 single dose, IV | 25 once daily | 18 | 0.99 (0.89, 1.11) | 1.08 (1.04, 1.13) | NC
Ledipasvir [Study conducted with ODEFSEY (FTC/RPV/TAF).] | 90/400 once daily | 25 once daily | 41 | 1.01 (0.97, 1.05) | 1.02 (0.97, 1.06) | 1.02 (0.98,1.07)
Sofosbuvir | 90/400 once daily | 25 once daily | 41 | 0.96 (0.89, 1.04) | 1.05 (1.01, 1.09) | NC
GS-331007, [The predominant circulating nucleoside metabolite of sofosbuvir.] | 90/400 once daily | 25 once daily | 41 | 1.08 (1.05, 1.11) | 1.08 (1.06, 1.10) | 1.10 (1.07, 1.12)
Norelgestromin | norgestimate 0.180/0.215/0.250 once daily/ethinyl estradiol 0.025 once daily | 25 once daily [Study conducted with FTC/TAF.] | 29 | 1.17 (1.07,1.26) | 1.12 (1.07, 1.17) | 1.16 (1.08,1.24)
Norgestrel | norgestimate 0.180/0.215/0.250 once daily/ethinyl estradiol 0.025 once daily | 25 once daily [Study conducted with FTC/TAF.] | 29 | 1.10 (1.02, 1.18) | 1.09 (1.01, 1.18) | 1.11 (1.03,1.20)
Ethinyl estradiol | norgestimate 0.180/0.215/0.250 once daily/ethinyl estradiol 0.025 once daily | 25 once daily [Study conducted with FTC/TAF.] | 29 | 1.22 (1.15, 1.29) | 1.11 (1.07, 1.16) | 1.02 (0.93,1.12)
CI=Confidence Interval; N=maximum number of subjects with data; NC=Not Calculated

12.4 Microbiology

Mechanism of Action

Emtricitabine: FTC, a synthetic nucleoside analog of cytidine, is phosphorylated by cellular enzymes to form emtricitabine 5'-triphosphate. Emtricitabine 5'-triphosphate inhibits the activity of the HIV-1 reverse transcriptase (RT) by competing with the natural substrate deoxycytidine 5'-triphosphate and by being incorporated into nascent viral DNA which results in chain termination. Emtricitabine 5′-triphosphate is a weak inhibitor of mammalian DNA polymerases α, β, Ɛ, and mitochondrial DNA polymerase γ.

Rilpivirine: RPV is a diarylpyrimidine non-nucleoside reverse transcriptase inhibitor of HIV-1 and inhibits HIV-1 replication by non-competitive inhibition of HIV-1 RT. RPV does not inhibit the human cellular DNA polymerases α, β, and mitochondrial DNA polymerase γ.

Tenofovir Alafenamide: TAF is a phosphonamidate prodrug of tenofovir (2'-deoxyadenosine monophosphate analog). Plasma exposure to TAF allows for permeation into cells and then TAF is intracellularly converted to tenofovir through hydrolysis by cathepsin A. Tenofovir is subsequently phosphorylated by cellular kinases to the active metabolite tenofovir diphosphate. Tenofovir diphosphate inhibits HIV-1 replication through incorporation into viral DNA by the HIV reverse transcriptase, which results in DNA chain termination.

Tenofovir has activity against human immunodeficiency virus (HIV-1). Cell culture studies have shown that both tenofovir and FTC can be fully phosphorylated when combined in cells. Tenofovir diphosphate is a weak inhibitor of mammalian DNA polymerases that include mitochondrial DNA polymerase γ and there is no evidence of toxicity to mitochondria cell culture.

Antiviral Activity in Cell Culture

Emtricitabine, Rilpivirine, and Tenofovir Alafenamide: The combinations of FTC, RPV, and TAF were not antagonistic with each other in cell culture combination antiviral activity assays. In addition, FTC, RPV, and TAF were not antagonistic with a panel of representatives from the major classes of approved anti-HIV agents (NNRTIs, NRTIs, INSTIs, and PIs).

Emtricitabine: The antiviral activity of FTC against laboratory and clinical isolates of HIV-1 was assessed in T lymphoblastoid cell lines, the MAGI-CCR5 cell line, and primary peripheral blood mononuclear cells (PBMCs). The EC50 values for FTC were in the range of 0.0013–0.64 microM. FTC displayed antiviral activity in cell culture against HIV-1 clades A, B, C, D, E, F, and G (EC50 values ranged from 0.007–0.075 microM) and showed strain-specific activity against HIV-2 (EC50 values ranged from 0.007–1.5 microM).

Rilpivirine: RPV exhibited activity against laboratory strains of wild-type HIV-1 in an acutely infected T-cell line with a median EC50 value for HIV-1IIIB of 0.73 nM. RPV demonstrated limited activity in cell culture against HIV-2 with a median EC50 value of 5220 nM (range 2510–10,830 nM). RPV demonstrated antiviral activity against a broad panel of HIV-1 group M (subtype A, B, C, D, F, G, H) primary isolates with EC50 values ranging from 0.07–1.01 nM and was less active against group O primary isolates with EC50 values ranging from 2.88–8.45 nM.

Tenofovir Alafenamide: The antiviral activity of TAF against laboratory and clinical isolates of HIV-1 subtype B was assessed in lymphoblastoid cell lines, PBMCs, primary monocyte/macrophage cells and CD4-T lymphocytes. The EC50 values for TAF ranged from 2.0–14.7 nM.

TAF displayed antiviral activity in cell culture against all HIV-1 groups (M, N, O), including sub-types A, B, C, D, E, F, and G (EC50 values ranged from 0.10–12.0 nM) and strain specific activity against HIV-2 (EC50 values ranged from 0.91–2.63 nM).

Resistance

In Cell Culture

Emtricitabine: HIV-1 isolates with reduced susceptibility to FTC were selected in cell culture. Reduced susceptibility to FTC was associated with M184V or I substitutions in HIV-1 RT.

Rilpivirine: RPV-resistant strains were selected in cell culture starting from wild-type HIV-1 of different origins and subtypes as well as NNRTI-resistant HIV-1. The frequently observed amino acid substitutions that emerged and conferred decreased phenotypic susceptibility to RPV included: L100I, K101E, V106I and A, V108I, E138K and G, Q, R, V179F and I, Y181C and I, V189I, G190E, H221Y, F227C, and M230I and L.

Tenofovir Alafenamide: HIV-1 isolates with reduced susceptibility to TAF were selected in cell culture. HIV-1 isolates selected by TAF expressed a K65R substitution in HIV-1 RT, sometimes in the presence of S68N or L429I substitutions; in addition, a K70E substitution in HIV-1 RT was observed.

In Clinical Trials

In HIV-1-Infected Subjects With No Antiretroviral Treatment History

Emtricitabine and Tenofovir Alafenamide: The resistance profile of ODEFSEY for the treatment of HIV-1 infection is based on studies of FTC+TAF with EVG+COBI in the treatment of HIV-1 infection. In a pooled analysis of antiretroviral-naïve subjects, genotyping was performed on plasma HIV-1 isolates from all subjects with HIV-1 RNA greater than 400 copies per mL at confirmed virologic failure, at Week 48, or at time of early study drug discontinuation. Genotypic resistance developed in 7 of 14 evaluable subjects. The resistance–associated substitutions that emerged were M184V/I (N=7) and K65R (N=1). Three subjects had virus with emergent R, H, or E at the polymorphic Q207 residue in reverse transcriptase.

Rilpivirine: In the Week 96 pooled resistance analysis for adult subjects receiving RPV or efavirenz in combination with FTC/TDF, the emergence of resistance was greater among subjects' viruses in the RPV+FTC/TDF arm compared to the efavirenz + FTC/TDF arm and was dependent on baseline viral load. In the Week 96 resistance analysis, 14% (77/550) of the subjects in the RPV+FTC/TDF arm and 8% (43/546) of the subjects in the efavirenz + FTC/TDF arm qualified for resistance analysis; 61% (47/77) of the subjects who qualified for resistance analysis (resistance-analysis subjects) in the RPV+FTC/TDF arm had virus with genotypic and/or phenotypic resistance to RPV compared to 42% (18/43) of the resistance-analysis subjects in the efavirenz + FTC/TDF arm who had genotypic and/or phenotypic resistance to efavirenz. Moreover, genotypic and/or phenotypic resistance to emtricitabine or tenofovir emerged in viruses from 57% (44/77) of the resistance-analysis subjects in the RPV arm compared to 26% (11/43) in the efavirenz arm.

Emerging NNRTI substitutions in the RPV resistance analysis of subjects' viruses included V90I, K101E/P/T, E138K/A/Q/G, V179I/L, Y181C/I, V189I, H221Y, F227C/L, and M230L, which were associated with an RPV phenotypic fold change range of 2.6–621. The E138K substitution emerged most frequently during RPV treatment, commonly in combination with the M184I substitution. The emtricitabine and lamivudine resistance-associated substitutions M184I or V and NRTI resistance-associated substitutions (K65R/N, A62V, D67N/G, K70E, Y115F, K219E/R) emerged more frequently in the RPV resistance-analysis subjects than in efavirenz resistance-analysis subjects.

NNRTI- and NRTI-resistance substitutions emerged less frequently in the resistance analysis of viruses from subjects with baseline viral loads of less than or equal to 100,000 copies/mL compared to viruses from subjects with baseline viral loads of greater than 100,000 copies/mL: 23% (10/44) compared to 77% (34/44) of NNRTI-resistance substitutions and 20% (9/44) compared to 80% (35/44) of NRTI-resistance substitutions. This difference was also observed for the individual emtricitabine/lamivudine and tenofovir resistance substitutions: 22% (9/41) compared to 78% (32/41) for M184I/V and 0% (0/8) compared to 100% (8/8) for K65R/N. Additionally, NNRTI and/or NRTI-resistance substitutions emerged less frequently in the resistance analysis of the viruses from subjects with baseline CD4+ cell counts greater than or equal to 200 cells/mm^3 compared to the viruses from subjects with baseline CD4+ cell counts less than 200 cells/mm^3: 32% (14/44) compared to 68% (30/44) of NNRTI-resistance substitutions and 27% (12/44) compared to 73% (32/44) of NRTI-resistance substitutions.

In Virologically-Suppressed Subjects

Emtricitabine and Tenofovir Alafenamide: One subject was identified with emergent resistance to FTC or TAF (M184M/I) out of 4 virologic failure subjects in a clinical study of virologically-suppressed subjects who switched from a regimen containing FTC+TDF to FTC+TAF with EVG+COBI (N=799).

Rilpivirine: Through Week 48, 4 subjects who switched their protease inhibitor-based regimen to FTC/RPV/TDF (4 of 469 subjects, 0.9%) and 1 subject who maintained their regimen (1 of 159 subjects, 0.6%) developed genotypic and/or phenotypic resistance to a study drug. All 4 of the subjects who had resistance emergence on FTC/RPV/TDF had evidence of FTC resistance and 3 of the subjects had evidence of RPV resistance.

ODEFSEY: Through Week 48, in subjects who switched to ODEFSEY from FTC/RPV/TDF or EFV/FTC/TDF (Trials 1216 (N=316) and 1160 (N=438), respectively), of seven subjects who developed virologic failure, three subjects had detectable NNRTI and/or NRTI resistance substitutions at virologic failure that were pre-existing in the baseline sample by proviral DNA sequencing; one of these subjects resuppressed while maintaining ODEFSEY.

Cross-Resistance

Emtricitabine: FTC-resistant viruses with the M184V/I substitution were cross-resistant to lamivudine, but retained sensitivity to didanosine, stavudine, tenofovir, and zidovudine.

Viruses harboring substitutions conferring reduced susceptibility to stavudine and zidovudine—thymidine analog substitutions (M41L, D67N, K70R, L210W, T215Y/F, K219Q/E), or didanosine (L74V) remained sensitive to FTC. HIV-1 containing the K103N substitution or other substitutions associated with resistance to NNRTIs was susceptible to FTC.

Rilpivirine: Considering all of the available cell culture and clinical data, any of the following amino acid substitutions, when present at baseline, are likely to decrease the antiviral activity of RPV: K101E, K101P, E138A, E138G, E138K, E138R, E138Q, V179L, Y181C, Y181I, Y181V, Y188L, H221Y, F227C, M230I, M230L, and the combination of L100I+K103N.

Cross-resistance in site-directed mutant virus has been observed among NNRTIs. The single NNRTI substitutions K101P, Y181I, and Y181V conferred 52 times, 15 times, and 12 times decreased susceptibility to RPV, respectively. The combination of E138K and M184I showed 6.7 times reduced susceptibility to RPV compared to 2.8 times for E138K alone. The K103N substitution did not show reduced susceptibility to RPV by itself. However, the combination of K103N and L100I resulted in a 7 times reduced susceptibility to RPV. In another study, the Y188L substitution resulted in a reduced susceptibility to RPV of 9 times for clinical isolates and 6 times for site-directed mutants. Combinations of 2 or 3 NNRTI resistance-associated substitutions gave decreased susceptibility to RPV (fold change range of 3.7–554) in 38% and 66% of mutants, respectively.

Cross-resistance to efavirenz, etravirine, and/or nevirapine is likely after virologic failure and development of RPV resistance.

Tenofovir Alafenamide: Tenofovir resistance substitutions K65R and K70E result in reduced susceptibility to abacavir, didanosine, emtricitabine, lamivudine, and tenofovir.

HIV-1 with multiple thymidine analog substitutions (M41L, D67N, K70R, L210W, T215F/Y, K219Q/E/N/R), or multinucleoside resistant HIV-1 with a T69S double insertion mutation or with a Q151M substitution complex including K65R showed reduced susceptibility to TAF in cell culture.

13 NONCLINICAL TOXICOLOGY

13.1 Carcinogenesis, Mutagenesis, Impairment of Fertility

Emtricitabine: In long-term carcinogenicity studies of FTC, no drug-related increases in tumor incidence were found in mice at doses up to 750 mg per kg per day (23 times the human systemic exposure at the recommended dose of 200 mg per day in ODEFSEY) or in rats at doses up to 600 mg per kg per day (28 times the human systemic exposure at the recommended dose in ODEFSEY).

FTC was not genotoxic in the reverse mutation bacterial test (Ames test), mouse lymphoma or mouse micronucleus assays.

FTC did not affect fertility in male rats at approximately 140 times or in male and female mice at approximately 60 times higher exposures (AUC) than in humans given the recommended 200 mg daily dose in ODEFSEY. Fertility was normal in the offspring of mice exposed daily from before birth (in utero) through sexual maturity at daily exposures (AUC) of approximately 60 times higher than human exposures at the recommended 200 mg daily dose in ODEFSEY.

Rilpivirine: RPV was evaluated for carcinogenic potential by oral gavage administration to mice and rats up to 104 weeks. Daily doses of 20, 60, and 160 mg per kg per day were administered to mice and doses of 40, 200, 500, and 1500 mg per kg per day were administered to rats. In rats, there were no drug-related neoplasms. In mice, RPV was positive for hepatocellular neoplasms in both males and females. The observed hepatocellular findings in mice may be rodent-specific. At the lowest tested doses in the carcinogenicity studies, the systemic exposures (based on AUC) to RPV were 21 times (mice) and 3 times (rats) relative to those observed in humans at the recommended dose (25 mg once daily) in ODEFSEY.

RPV has tested negative in the absence and presence of a metabolic activation system, in the in vitro Ames reverse mutation assay and in vitro clastogenicity mouse lymphoma assay. RPV did not induce chromosomal damage in the in vivo micronucleus test in mice.

In a study conducted in rats, there were no effects on mating or fertility with RPV up to 400 mg per kg per day, a dose of RPV that showed maternal toxicity. This dose is associated with an exposure that is approximately 40 times higher than the exposure in humans at the recommended dose of 25 mg once daily in ODEFSEY.

Tenofovir Alafenamide: Since TAF is rapidly converted to tenofovir and a lower tenofovir exposure in rats and mice was observed after TAF administration compared to TDF administration, carcinogenicity studies were conducted only with TDF. Long-term oral carcinogenicity studies of TDF in mice and rats were carried out at exposures up to approximately 10 times (mice) and 4 times (rats) those observed in humans at the recommended dose of TDF (300 mg) for HIV-1 infection. The tenofovir exposure in these studies was approximately 167 times (mice) and 55 times (rat) those observed in humans after administration of the daily recommended dose of ODEFSEY. At the high dose in female mice, liver adenomas were increased at tenofovir exposures approximately 10 times (300 mg TDF) and 167 times (ODEFSEY) the exposure observed in humans. In rats, the study was negative for carcinogenic findings.

TAF was not genotoxic in the reverse mutation bacterial test (Ames test), mouse lymphoma or rat micronucleus assays.

There were no effects on fertility, mating performance or early embryonic development when TAF was administered to male rats at a dose equivalent to 62 times the human dose based on body surface area comparisons for 28 days prior to mating and to female rats for 14 days prior to mating through Day 7 of gestation.

13.2 Animal Toxicology and/or Pharmacology

Minimal to slight infiltration of mononuclear cells in the posterior uvea was observed in dogs with similar severity after three- and nine-month administration of TAF; reversibility was seen after a three-month recovery period. No eye toxicity was observed in the dog at systemic exposures of 5 (TAF) and 15 (tenofovir) times the exposure seen in humans at the recommended daily TAF dose in ODEFSEY.

14 CLINICAL STUDIES

14.1 Clinical Trial Results in HIV-1 Virologically-Suppressed Subjects Who Switched to ODEFSEY

In Trial 1216, the efficacy and safety of switching from emtricitabine/rilpivirine/tenofovir disoproxil fumarate (FTC/RPV/TDF) to ODEFSEY were evaluated in a randomized, double-blind study of virologically-suppressed HIV-1 infected adults. Subjects were suppressed (HIV-1 RNA <50 copies/mL) on their baseline regimen of FTC/RPV/TDF for at least 6 months and have no documented resistance mutations to FTC, TAF, or RPV prior to study entry. Subjects were randomized in a 1:1 ratio to either switch to ODEFSEY (N=316) once daily or stay on FTC/RPV/TDF (N=314) once daily. Subjects had a mean age of 45 years (range: 23–72), 90% were male, 75% were White, and 19% were Black. The mean baseline CD4+ cell count was 709 cells/mm^3 (range: 104–2527).

In Trial 1160, the efficacy and safety of switching from efavirenz/emtricitabine/tenofovir disoproxil fumarate (EFV/FTC/TDF) to ODEFSEY were evaluated in a randomized, double-blind study of virologically-suppressed HIV-1 infected adults. Subjects must have been stably suppressed (HIV-1 RNA <50 copies/mL) on their baseline regimen of EFV/FTC/TDF for at least 6 months and have no documented resistance mutations to FTC, TAF, or RPV prior to study entry. Subjects were randomized in a 1:1 ratio to either switch to ODEFSEY (N=438) once daily or stay on EFV/FTC/TDF (N=437) once daily. Subjects had a mean age of 48 years (range: 19–76), 87% were male, 67% were White, and 27% were Black. The mean baseline CD4+ cell count was 700 cells/mm^3 (range: 140–1862).

Treatment outcomes of Trials 1216 and 1160 are presented in Table 11.

Table 11 Virologic Outcomes of Trials 1216 and 1160 at Week 48 [Week 48 window was between Day 295 and 378 (inclusive).] in Virologically-Suppressed Subjects who Switched to ODEFSEY
 | Study 1216 |  | Study 1160
 | ODEFSEY (N=316) | FTC/RPV/TDF (N=313) [One subject who was not on FTC/RPV/TDF prior to screening was excluded from the efficacy analysis.] | ODEFSEY (N=438) | EFV/FTC/TDF (N=437)
HIV-1 RNA <50 copies/mL | 94% | 94% | 90% | 92%
HIV-1 RNA ≥50 copies/mL [Included subjects who had HIV-1 RNA ≥50 copies/mL in the Week 48 window; subjects who discontinued early due to lack or loss of efficacy; subjects who discontinued for reasons other than lack or loss of efficacy and at the time of discontinuation had a viral value of ≥50 copies/mL.] | 1% | 0% | 1% | 1%
No Virologic Data at Week 48 Window | 6% | 6% | 9% | 7%
Discontinued Study Drug Due to AE or Death and Last Available HIV-1 RNA <50 copies/mL | 2% | 1% | 3% | 1%
Discontinued Study Drug Due to Other Reasons and Last Available HIV-1 RNA <50 copies/mL [Includes subjects who discontinued for reasons other than an AE, death, or lack or loss of efficacy; e.g., withdrew consent, loss to follow-up, etc.] | 4% | 4% | 5% | 5%
Missing Data During Window but on Study Drug | <1% | 1% | 1% | 1%

14.2 Clinical Trial Results for Subjects with no Antiretroviral Treatment History for Components of ODEFSEY

The efficacy of RPV, FTC, and TAF in the treatment of HIV-1 infection in adults as initial therapy in those with no antiretroviral treatment history [see Indications and Usage (1)] was established in trials of:

- RPV+FTC/TDF in HIV-1 infected adults as initial therapy in those with no antiretroviral treatment history (n=550). The virologic response rate (i.e., HIV-1 RNA less than 50 copies per mL) was 77% at Week 96. The virologic response rate at 96 weeks was 83% in subjects with baseline HIV-1 RNA less than or equal to 100,000 copies per mL and 71% in subjects with baseline HIV-1 RNA greater than 100,000 copies per mL. Further, the virologic response rate at 96 weeks among subjects with baseline CD4+ cell counts less than 200 and greater than or equal to 200 cells/mm^3 were 68% and 82%, respectively.
- FTC+TAF with EVG+COBI in HIV-1 infected adults as initial therapy in those with no antiretroviral treatment history (n=866). The virologic response rate (i.e., HIV-1 RNA less than 50 copies per mL) was 92% at Week 48.

The efficacy of RPV, FTC, and TAF in the treatment of HIV-1 infection in pediatric patients aged 12 to less than 18 years old and greater than 32–35 kg as initial therapy in those with no antiretroviral treatment history and to replace a stable antiretroviral regimen in those who are virologically-suppressed [see Indications and Usage (1)] was established in trials of antiretroviral treatment-naïve HIV-1 infected pediatric subjects 12 to less than 18 years old with:

- RPV in combination with other antiretroviral agents in 36 treatment-naïve HIV-1 infected adolescents weighing at least 32 kg. The majority of subjects (24/36) received RPV in combination with FTC and TDF. Of these 24 subjects, 20 had a baseline HIV-1 RNA less than or equal to 100,000 copies per mL. The virologic response rate in these 20 subjects (i.e., HIV-1 RNA less than 50 copies per mL) was 80% (16/20) at 48 weeks.
- FTC+TAF with EVG+COBI in 23 adolescents weighing at least 35 kg. The virologic response rate (i.e., HIV-1 RNA less than 50 copies per mL) was 91% at 24 weeks.

In the clinical trial of 248 HIV-1 infected adult patients with estimated creatinine clearance greater than 30 mL per minute but less than 70 mL per minute, 95% (235/248) of the combined populations of treatment-naïve (N=6) begun on FTC+TAF with EVG+COBI and those previously virologically-suppressed on other regimens (N=242) and switched to FTC+TAF with EVG +COBI had HIV-RNA levels less than 50 copies per mL at Week 24.

16 HOW SUPPLIED/STORAGE AND HANDLING

Product: 50090-2340

NDC: 50090-2340-0 30 TABLET in a BOTTLE, PLASTIC

17 PATIENT COUNSELING INFORMATION

Advise the patient to read the FDA-approved patient labeling (Patient Information).

Post-treatment Acute Exacerbation of Hepatitis B in Patients with HBV Coinfection

Severe acute exacerbations of hepatitis B have been reported in patients who are coinfected with HBV and HIV-1 and have discontinued products containing FTC and/or TDF, and may likewise occur with discontinuation of ODEFSEY [see Warnings and Precautions (5.1)]. Advise the patient to not discontinue ODEFSEY without first informing their healthcare provider.

Severe Skin Reactions and Hypersensitivity

Inform patients that skin reactions ranging from mild to severe, including Drug Reaction with Eosinophilia and Systemic Symptoms (DRESS), have been reported with RPV-containing products. Instruct patients to immediately stop taking ODEFSEY and seek medical attention if they develop a rash associated with any of the following symptoms: fever, blisters, mucosal involvement, eye inflammation (conjunctivitis), severe allergic reaction causing swelling of the face, eyes, lips, mouth, tongue or throat which may lead to difficulty swallowing or breathing, and any signs and symptoms of liver problems, as they may be a sign of a more serious reaction. Patients should understand that if severe rash occurs, they will be closely monitored, laboratory tests will be performed and appropriate therapy will be initiated [see Warnings and Precautions (5.2)].

Drug Interactions

ODEFSEY may interact with many drugs and is not recommended to be coadministered with numerous drugs. Advise patients to report to their healthcare provider the use of any other prescription or nonprescription medication or herbal products, including St. John's wort [see Contraindications (4), Warnings and Precautions (5.3) and Drug Interactions (7)].

Depressive Disorders

Inform patients that depressive disorders (depressed mood, depression, dysphoria, major depression, mood altered, negative thoughts, suicide attempt, suicidal ideation) have been reported with RPV. Inform patients to seek immediate medical evaluation if they experience depressive symptoms [see Warnings and Precautions (5.5)].

Hepatotoxicity

Inform patients that hepatotoxicity has been reported with RPV, therefore, it is important to inform the healthcare professional if patients have underlying hepatitis B or C or elevations in liver-associated tests prior to treatment [see Dosage and Administration (2.1) and Warnings and Precautions (5.6)].

Immune Reconstitution Syndrome

Advise patients to inform their healthcare provider immediately of any symptoms of infection, as in some patients with advanced HIV infection (AIDS), signs and symptoms of inflammation from previous infections may occur soon after anti-HIV treatment is started [see Warnings and Precautions (5.7)].

New Onset or Worsening Renal Impairment

Advise patients to avoid taking ODEFSEY with concurrent or recent use of nephrotoxic agents. Renal impairment, including cases of acute renal failure, has been reported in association with the use of tenofovir prodrugs [see Warnings and Precautions (5.8)].

Lactic Acidosis and Severe Hepatomegaly

Lactic acidosis and severe hepatomegaly with steatosis, including fatal cases, have been reported with use of drugs similar to ODEFSEY. Advise patients to stop taking ODEFSEY if they develop clinical symptoms suggestive of lactic acidosis or pronounced hepatotoxicity [see Warnings and Precautions (5.9)].

Missed Dosage

Inform patients that it is important to take ODEFSEY on a regular dosing schedule with a meal and to avoid missing doses, as it can result in development of resistance [see Dosage and Administration (2.2)].

Pregnancy Registry

Inform patients that there is an antiretroviral pregnancy registry to monitor fetal outcomes of pregnant women exposed to ODEFSEY [see Use in Specific Populations (8.1)].

Lactation

Instruct women with HIV-1 infection not to breastfeed because HIV-1 can be passed to the baby in breast milk [see Use in Specific Populations (8.2)].

ODEFSEY is a trademark of Gilead Sciences, Inc., or its related companies. All other trademarks referenced herein are the property of their respective owners.

Patient Information
ODEFSEY® (oh-DEF-see)
(emtricitabine, rilpivirine and tenofovir alafenamide)
tablets

Important: Ask your healthcare provider or pharmacist about medicines that should not be taken with ODEFSEY. For more information, see "What should I tell my healthcare provider before taking ODEFSEY?"

What is the most important information I should know about ODEFSEY?

ODEFSEY can cause serious side effects, including:

Worsening of Hepatitis B virus infection. ODEFSEY is not for use to treat chronic hepatitis B virus (HBV) infection. If you have hepatitis B virus (HBV) infection and take ODEFSEY, your HBV may get worse (flare-up) if you stop taking ODEFSEY. A "flare-up" is when your HBV infection suddenly returns in a worse way than before.

- Do not run out of ODEFSEY. Refill your prescription or talk to your healthcare provider before your ODEFSEY is all gone.
- Do not stop taking ODEFSEY without first talking to your healthcare provider.
- If you stop taking ODEFSEY, your healthcare provider will need to check your health often and do blood tests regularly for several months to check your HBV infection. Tell your healthcare provider about any new or unusual symptoms you may have after you stop taking ODEFSEY.

For more information about side effects, see "What are the possible side effects of ODEFSEY?"

What is ODEFSEY?

ODEFSEY is a prescription medicine that is used to treat Human Immunodeficiency Virus-1 (HIV-1) in people 12 years of age and older:

- who have not received anti-HIV-1 medicines in the past and who have an amount of HIV-1 in their blood (this is called "viral load") that is no more than 100,000 copies/mL, or
- to replace their current anti-HIV-1 medicines for people whose healthcare provider determines that they meet certain requirements.

HIV-1 is the virus that causes AIDS (Acquired Immune Deficiency Syndrome).

ODEFSEY contains the prescription medicines emtricitabine, rilpivirine and tenofovir alafenamide.

It is not known if ODEFSEY is safe and effective in children under 12 years of age or who weigh less than 77 lb (35 kg).

Who should not take ODEFSEY?

Do not take ODEFSEY if you also take a medicine that contains:

- carbamazepine (CARBATROL®, EPITOL®, EQUETRO®, TEGRETOL®, TEGRETOL-XR®, TERIL®)
- dexamethasone (OZURDEX®, MAXIDEX®, DECADRON®, BAYCADRON™)
- dexlansoprazole (DEXILANT®)
- esomeprazole (NEXIUM®, VIMOVO®)
- lansoprazole (PREVACID®)
- omeprazole (PRILOSEC®, ZEGERID®)
- oxcarbazepine (TRILEPTAL®)
- pantoprazole sodium (PROTONIX®)
- phenobarbital (LUMINAL®)
- phenytoin (DILANTIN®, DILANTIN-125®, PHENYTEK®)
- rabeprazole (ACIPHEX®)
- rifampin (RIFADIN®, RIFAMATE®, RIFATER®, RIMACTANE®)
- rifapentine (PRIFTIN®)
- St. John's wort (Hypericum perforatum) or a product that contains St. John's wort

What should I tell my healthcare provider before taking ODEFSEY?

Before taking ODEFSEY, tell your healthcare provider about all your medical conditions, including if you:

- have liver problems, including hepatitis B or C virus infection
- have kidney problems
- have a history of depression or suicidal thoughts
- are pregnant or plan to become pregnant. It is not known if ODEFSEY can harm your unborn baby. Tell your healthcare provider if you become pregnant during treatment with ODEFSEY.
  Pregnancy Registry: There is a pregnancy registry for women who take ODEFSEY during pregnancy. The purpose of this registry is to collect information about the health of you and your baby. Talk with your healthcare provider about how you can take part in this registry.
- are breastfeeding or plan to breastfeed. Do not breastfeed if you take ODEFSEY.
  - You should not breastfeed if you have HIV-1 because of the risk of passing HIV-1 to your baby.
  - At least one of the medicines in ODEFSEY can pass to your baby in your breast milk. It is not known if the other medicines in ODEFSEY can pass into your breast milk.
  Talk with your healthcare provider about the best way to feed your baby during treatment with ODEFSEY.

Tell your healthcare provider about all the medicines you take, including prescription and over-the-counter medicines, vitamins, and herbal supplements.

Some medicines may interact with ODEFSEY. Keep a list of your medicines and show it to your healthcare provider and pharmacist when you get a new medicine.

- You can ask your healthcare provider or pharmacist for a list of medicines that interact with ODEFSEY.
- Do not start a new medicine without telling your healthcare provider. Your healthcare provider can tell you if it is safe to take ODEFSEY with other medicines.

How should I take ODEFSEY?

- Take ODEFSEY exactly as your healthcare provider tells you to take it. ODEFSEY is taken by itself (not with other HIV-1 medicines) to treat HIV-1 infection.
- Take ODEFSEY 1 time each day with a meal.
- Do not change your dose or stop taking ODEFSEY without first talking with your healthcare provider. Stay under a healthcare provider's care during treatment with ODEFSEY.
- Do not miss a dose of ODEFSEY.
- If you take too much ODEFSEY, call your healthcare provider or go to the nearest hospital emergency room right away.
- When your ODEFSEY supply starts to run low, get more from your healthcare provider or pharmacy. This is very important because the amount of virus in your blood may increase if the medicine is stopped for even a short time. The virus may develop resistance to ODEFSEY and become harder to treat.

What are the possible side effects of ODEFSEY?

ODEFSEY may cause serious side effects, including:

- See "What is the most important information I should know about ODEFSEY?"
- Severe skin rash and allergic reactions. Skin rash is a common side effect of ODEFSEY. Rash can be serious. Call your healthcare provider right away if you get a rash. In some cases, rash and allergic reaction may need to be treated in a hospital.
  If you get a rash with any of the following symptoms, stop taking ODEFSEY and call your healthcare provider or get medical help right away:

- fever
- skin blisters
- mouth sores
- redness or swelling of the eyes (conjunctivitis)

- swelling of the face, lips, mouth, or throat
- trouble breathing or swallowing
- pain on the right side of the stomach (abdominal) area
- dark "tea colored" urine

- Depression or mood changes. Tell your healthcare provider right away if you have any of the following symptoms:
  - feel sad or hopeless
  - feel anxious or restless
  - have thoughts of hurting yourself (suicide) or have tried to hurt yourself
- Change in liver enzymes. People with a history of hepatitis B or C virus infection or who have certain liver enzyme changes may have an increased risk of developing new or worsening liver problems during treatment with ODEFSEY. Liver problems can also happen during treatment with ODEFSEY in people without a history of liver disease. Your healthcare provider may need to do tests to check your liver enzymes before and during treatment with ODEFSEY.
- Changes in your immune system (Immune Reconstitution Syndrome) can happen when you start taking HIV-1 medicines. Your immune system may get stronger and begin to fight infections that have been hidden in your body for a long time. Tell your healthcare provider right away if you start having any new symptoms after starting your HIV-1 medicine.
- New or worse kidney problems, including kidney failure. Your healthcare provider should do blood and urine tests to check your kidneys before you start and during treatment with ODEFSEY. Your healthcare provider may tell you to stop taking ODEFSEY if you develop new or worse kidney problems.
- Too much lactic acid in your blood (lactic acidosis). Too much lactic acid is a serious but rare medical emergency that can lead to death. Tell your healthcare provider right away if you get these symptoms: weakness or being more tired than usual, unusual muscle pain, being short of breath or fast breathing, stomach pain with nausea and vomiting, cold or blue hands and feet, feel dizzy or lightheaded, or a fast or abnormal heartbeat.
- Severe liver problems. In rare cases, severe liver problems can happen that can lead to death. Tell your healthcare provider right away if you get these symptoms: skin or the white part of your eyes turns yellow, dark "tea-colored" urine, light-colored stools, loss of appetite for several days or longer, nausea, or stomach-area pain.

The most common side effects of ODEFSEY are headache and problems sleeping.

These are not all the possible side effects of ODEFSEY.

Call your doctor for medical advice about side effects. You may report side effects to FDA at 1-800-FDA-1088.

How should I store ODEFSEY?

- Store ODEFSEY below 86°F (30°C).
- Keep ODEFSEY in its original container.
- Keep the container tightly closed.

Keep ODEFSEY and all medicines out of reach of children.

General information about the safe and effective use of ODEFSEY.

Medicines are sometimes prescribed for purposes other than those listed in a Patient Information leaflet. Do not use ODEFSEY for a condition for which it was not prescribed. Do not give ODEFSEY to other people, even if they have the same symptoms you have. It may harm them.

You can ask your healthcare provider or pharmacist for information about ODEFSEY that is written for health professionals.

For more information, call 1-800-445-3235 or go to www.ODEFSEY.com.

What are the ingredients in ODEFSEY?

Active ingredients: emtricitabine, rilpivirine, and tenofovir alafenamide

Inactive ingredients: croscarmellose sodium, lactose monohydrate, magnesium stearate, microcrystalline cellulose, polysorbate 20, and povidone. The tablet film coating contains iron oxide black, polyethylene glycol, polyvinyl alcohol, talc, and titanium dioxide

Manufactured and distributed by: Gilead Sciences, Inc. Foster City, CA 94404

ODEFSEY is a trademark of Gilead Sciences, Inc., or its related companies. All other trademarks referenced herein are the property of their respective owners.

© 2017 Gilead Sciences, Inc. All rights reserved.

208351-GS-002

This Patient Information has been approved by the U.S. Food and Drug Administration

Revised: 08/2017